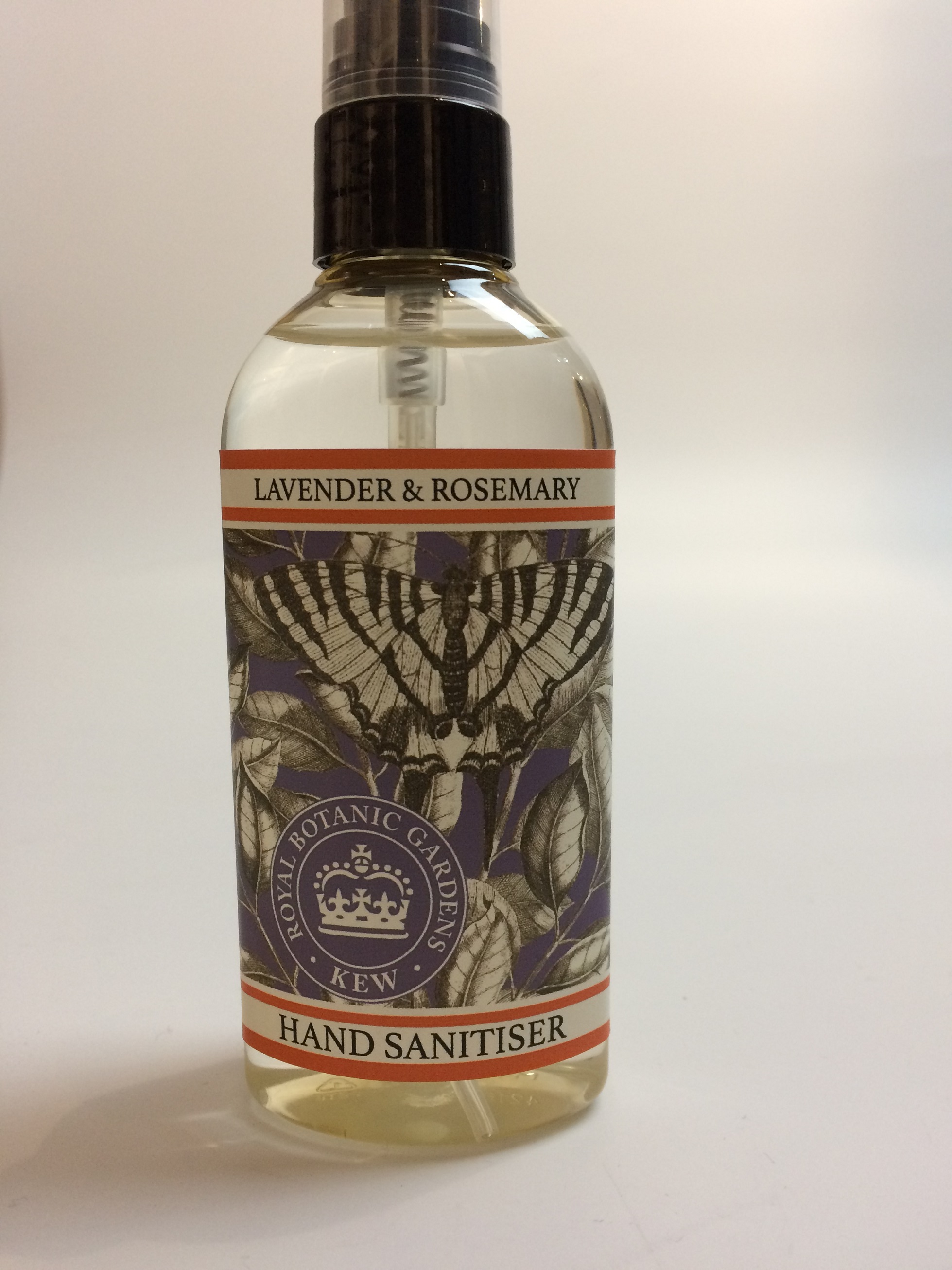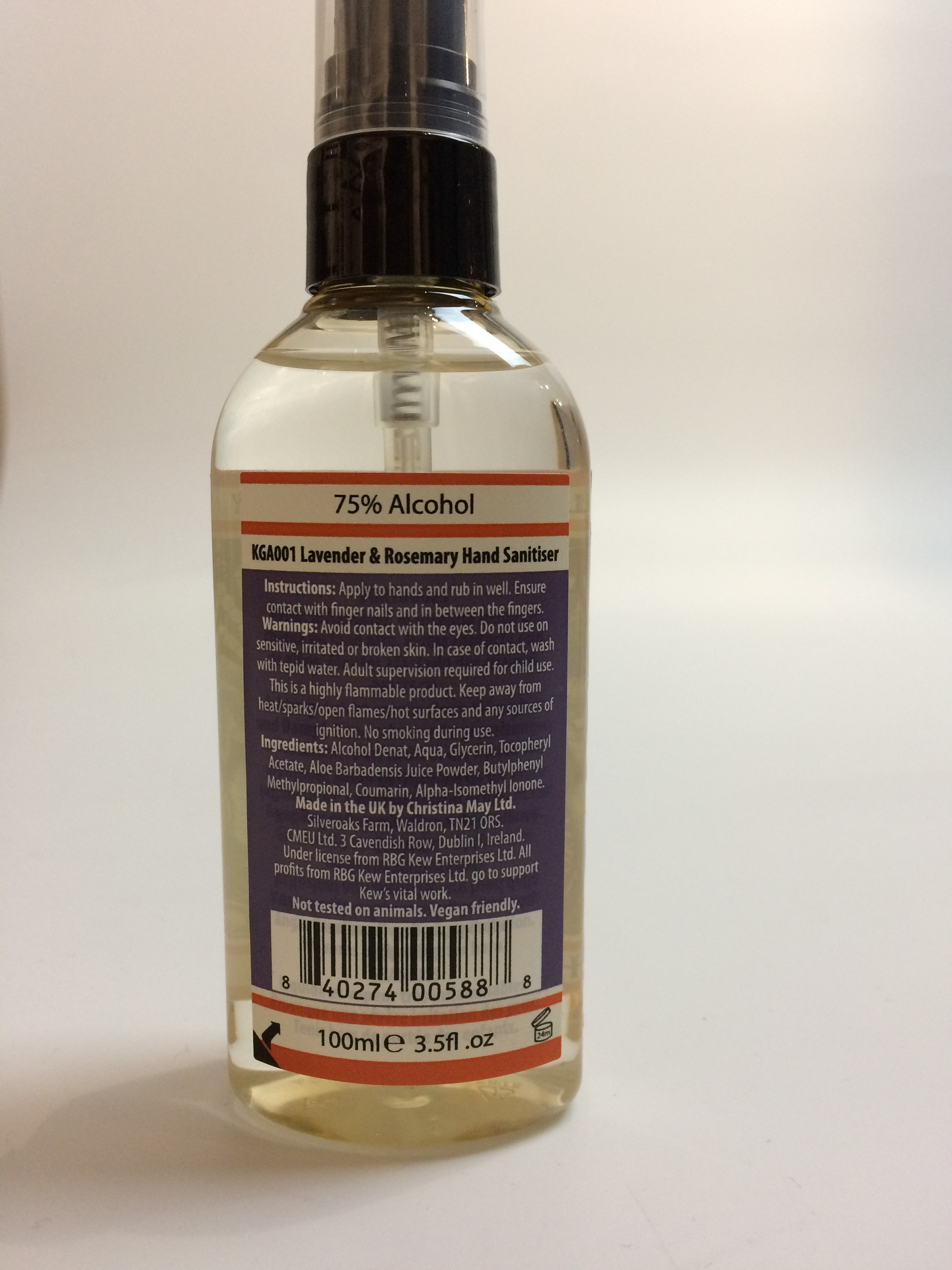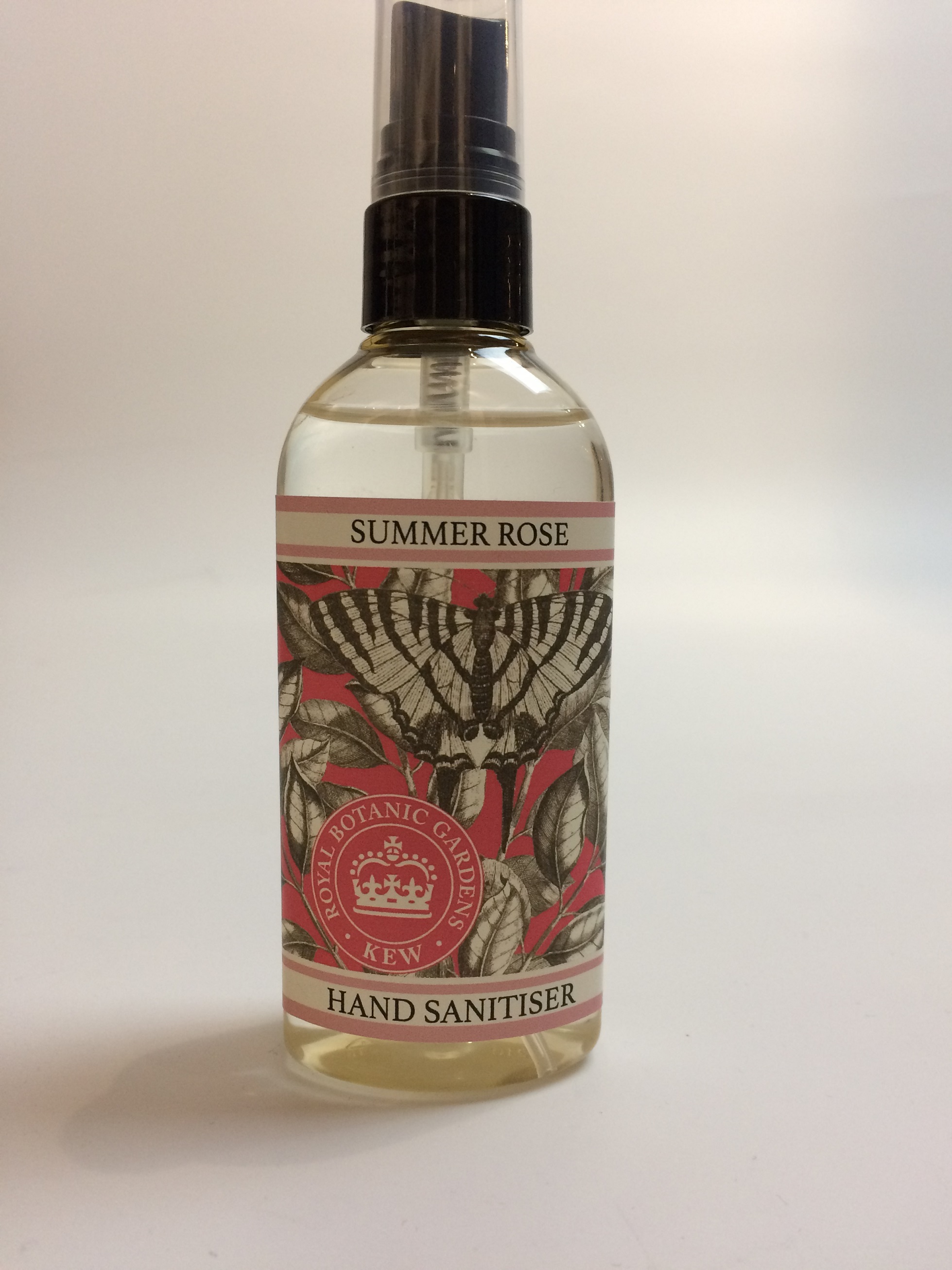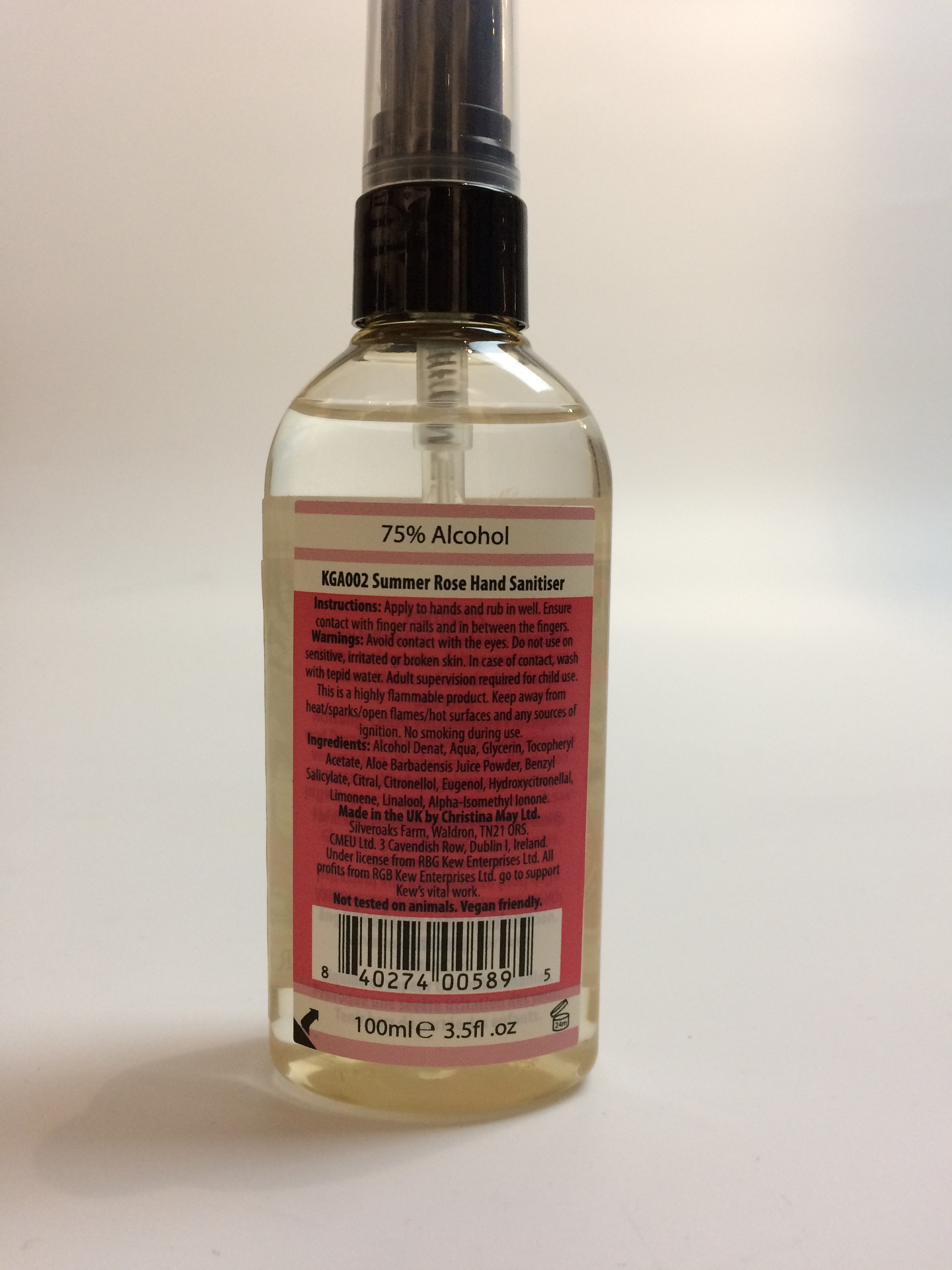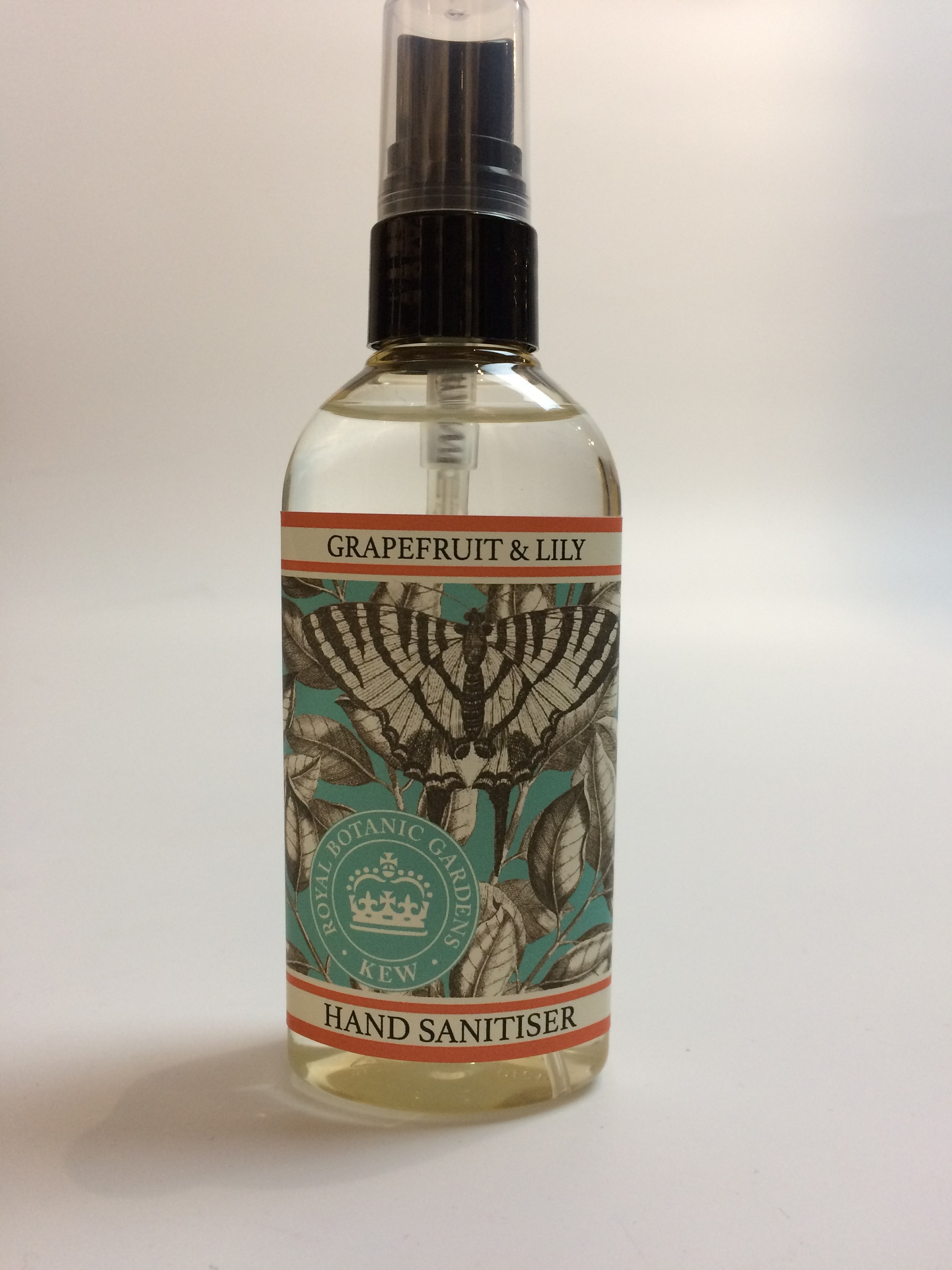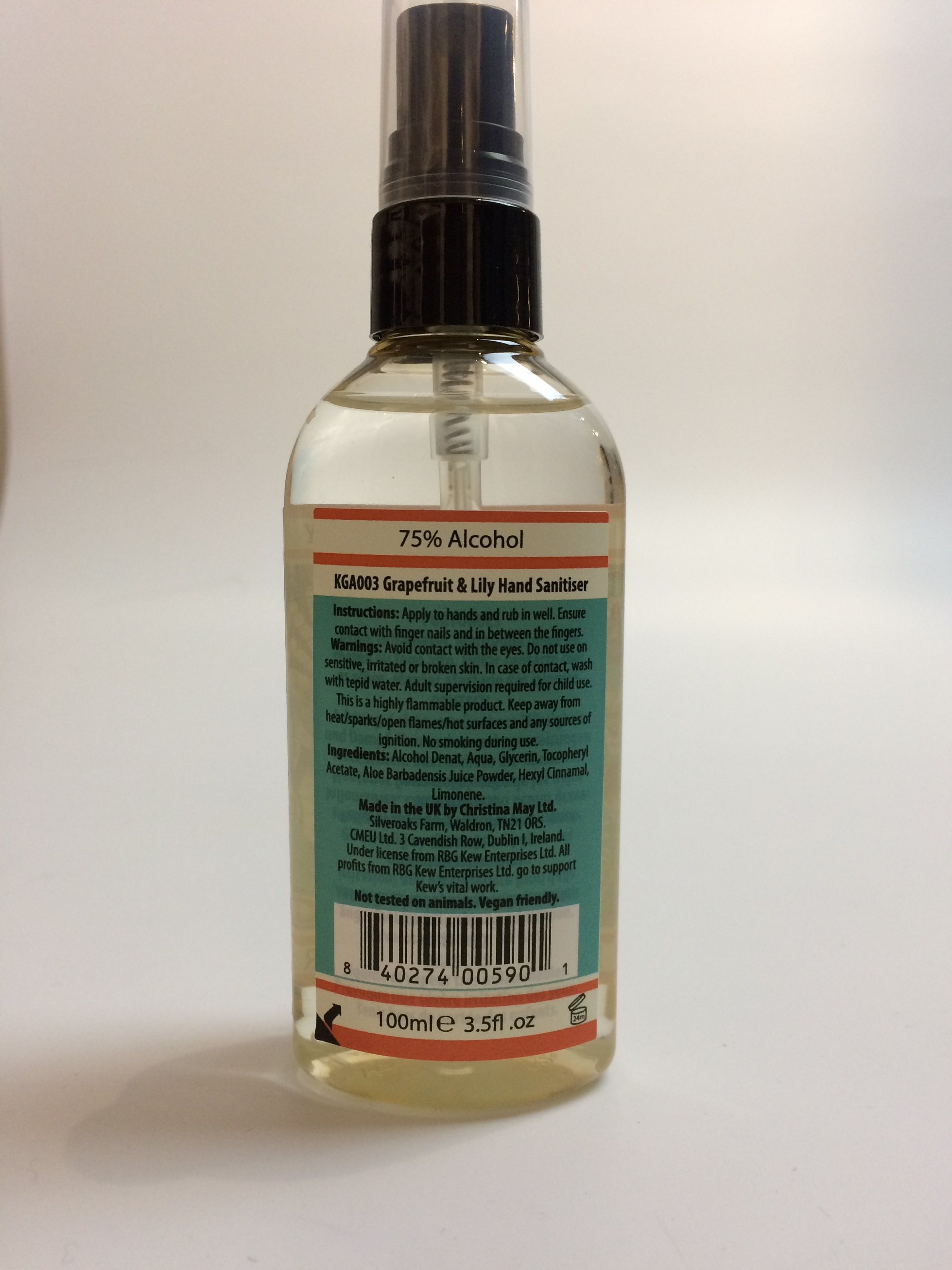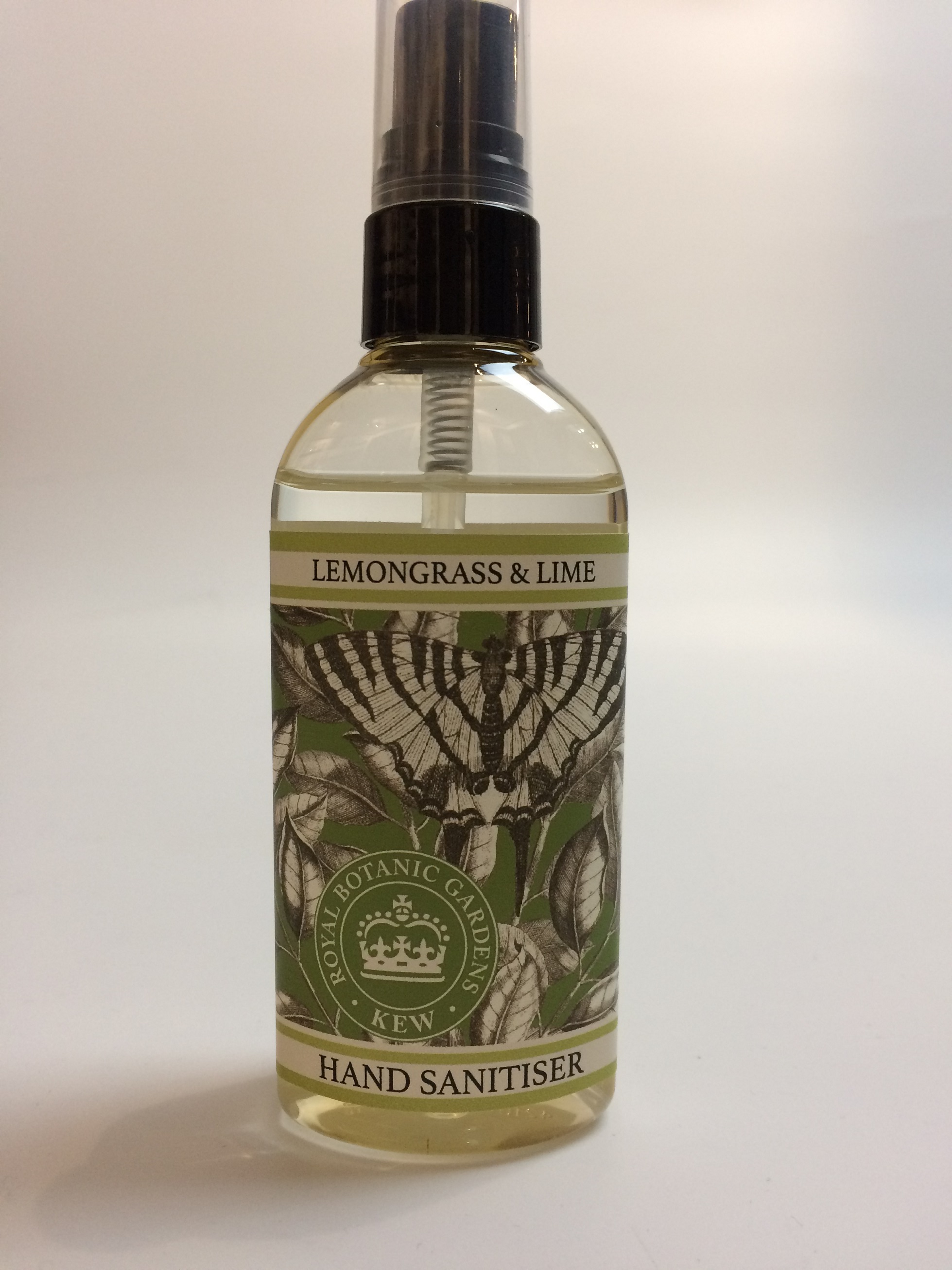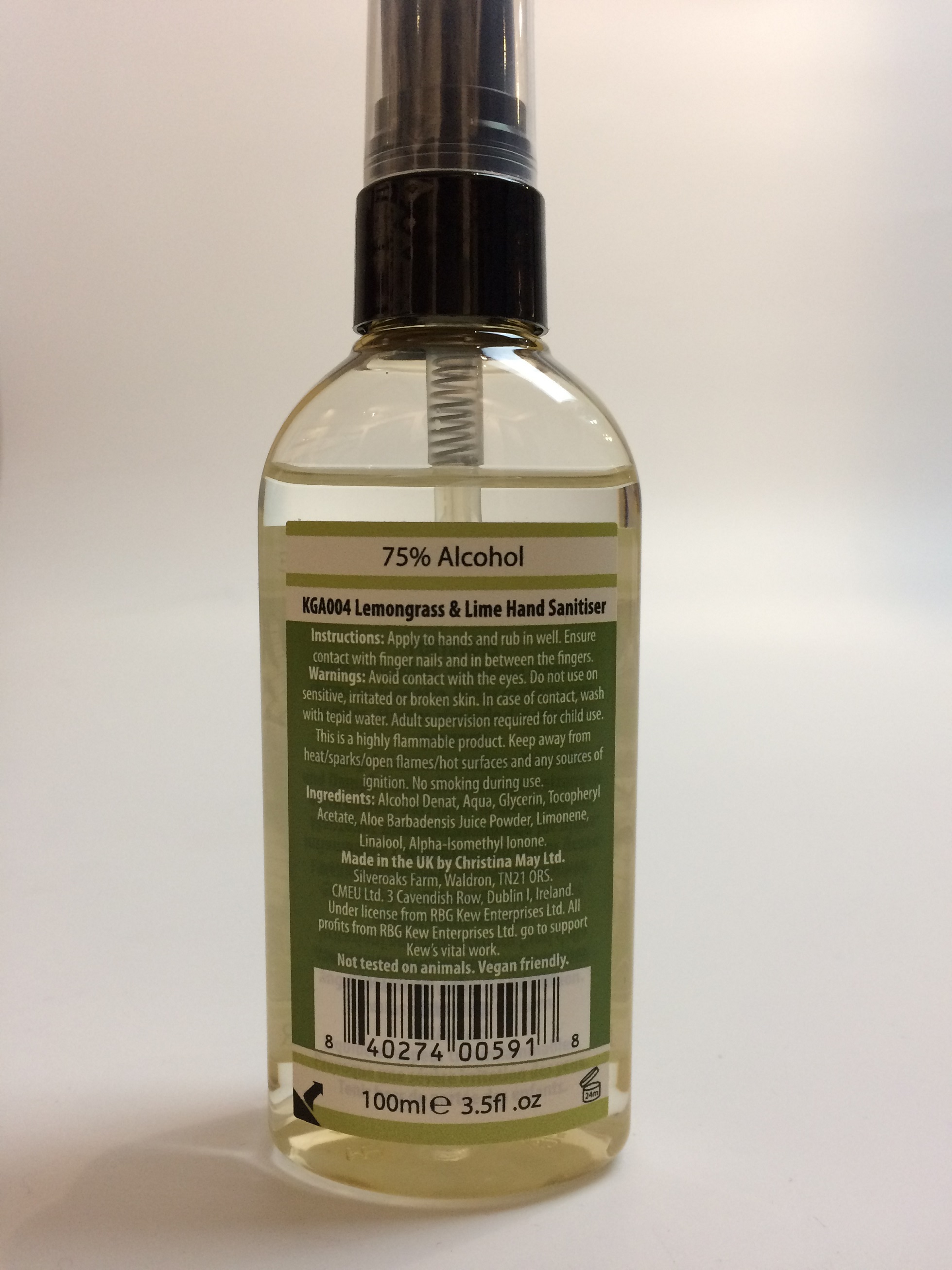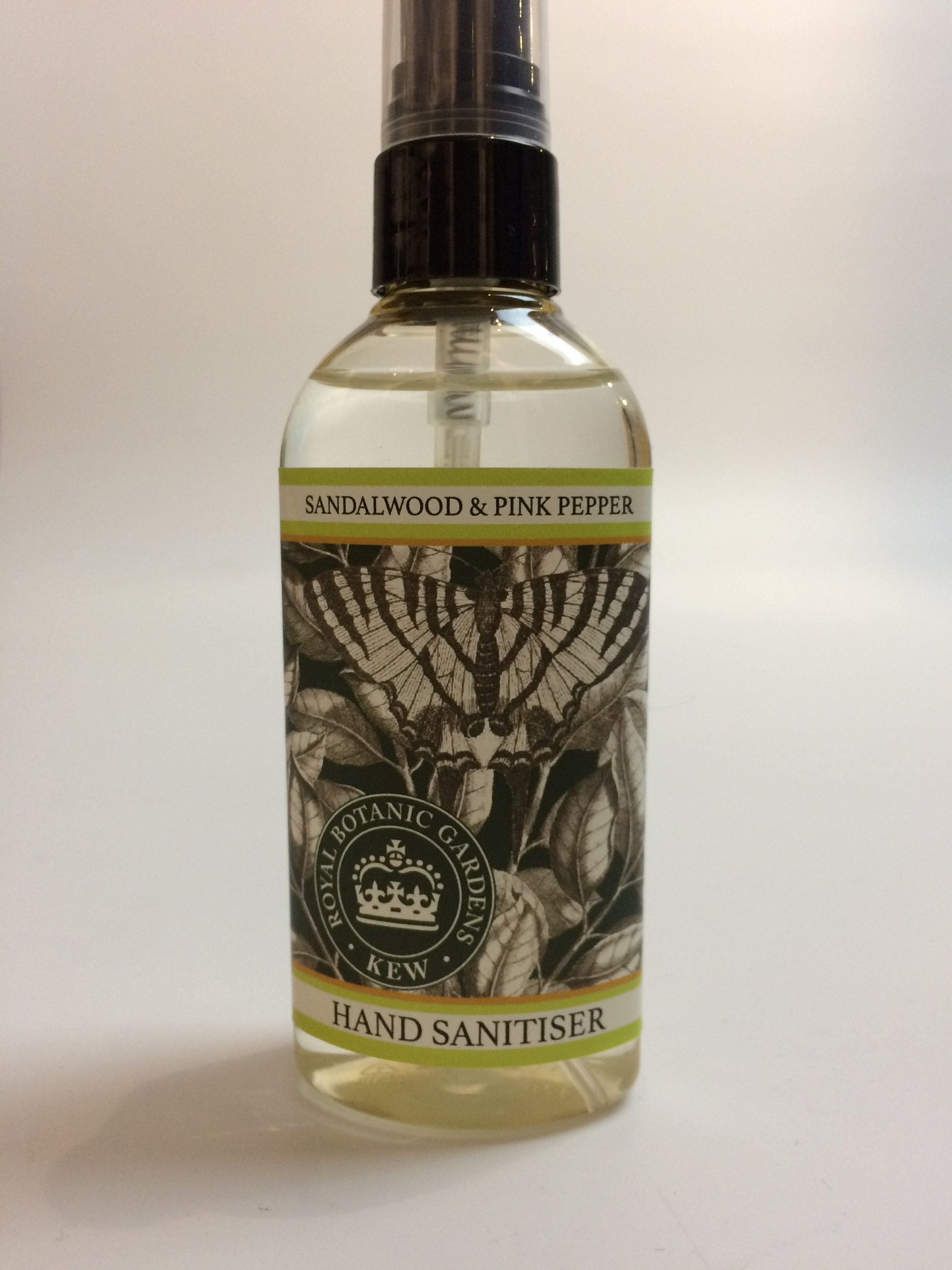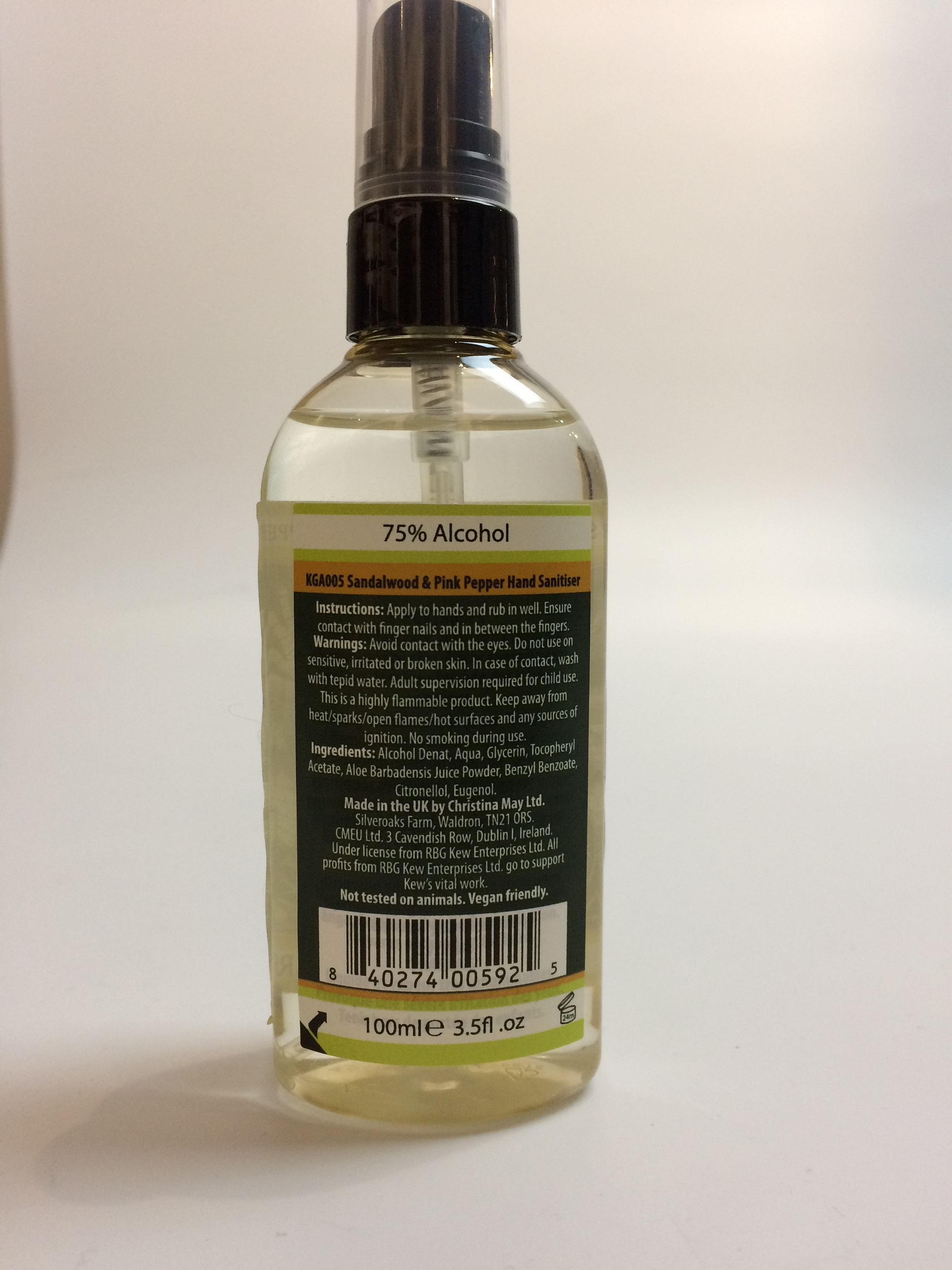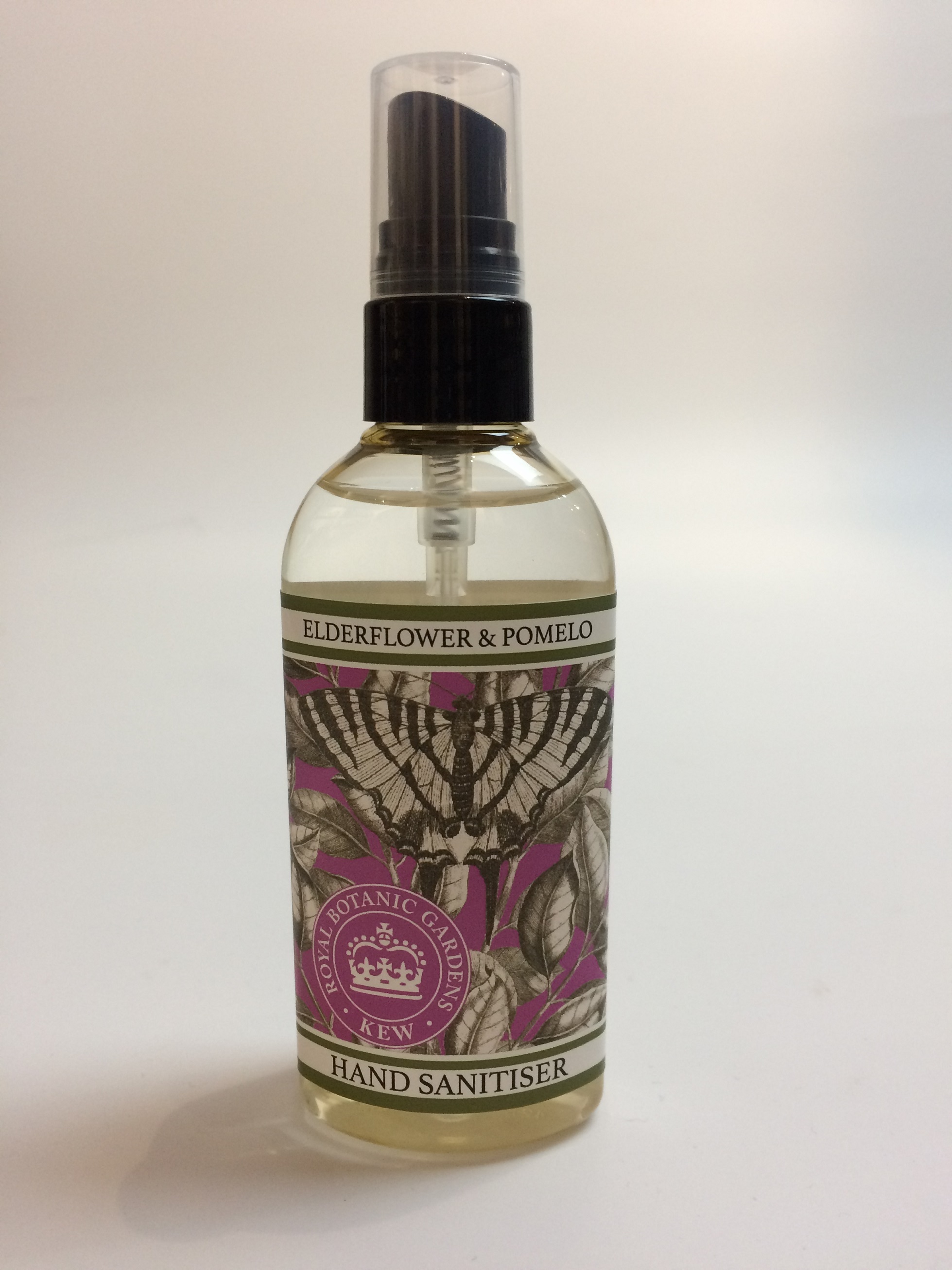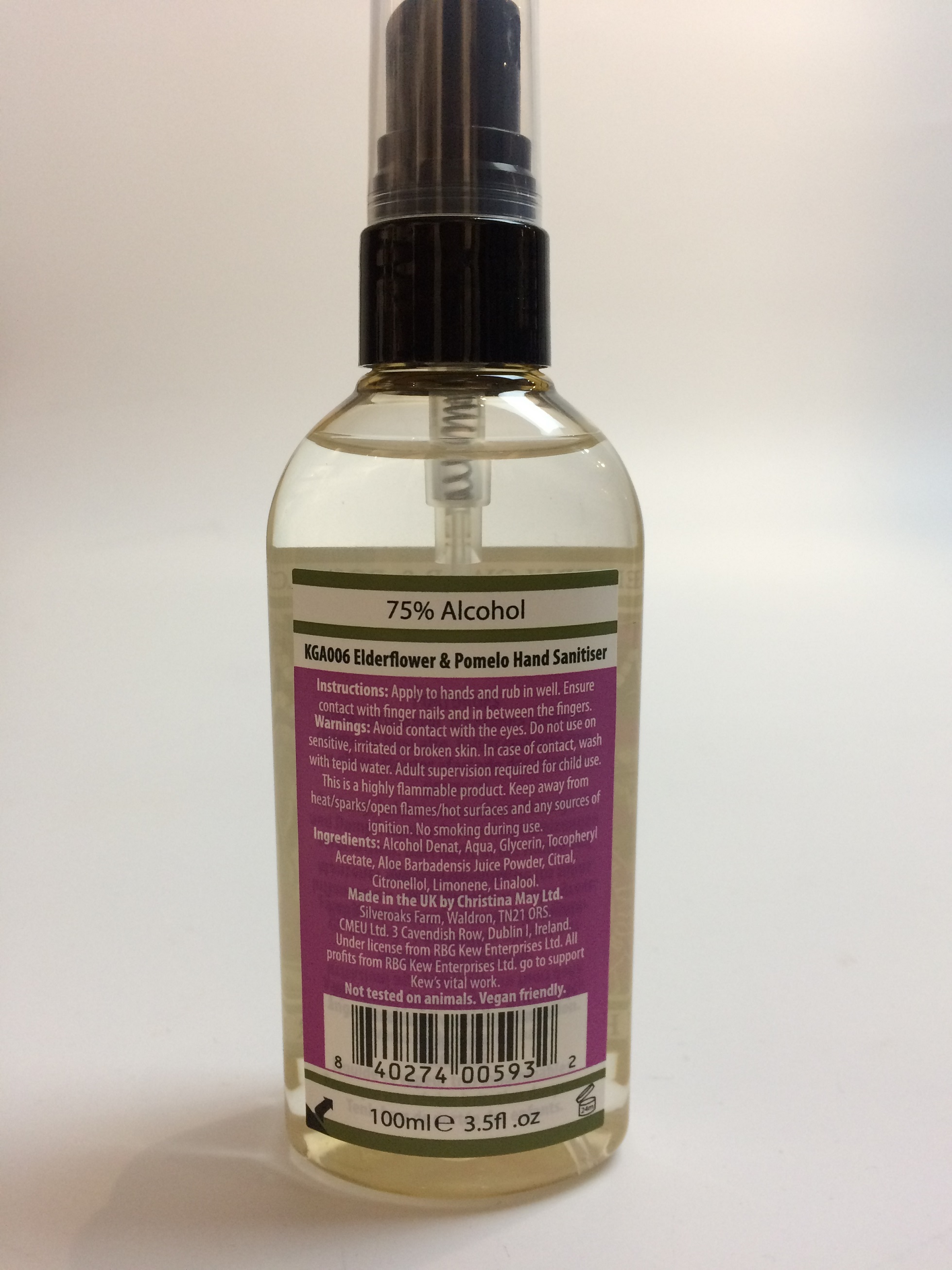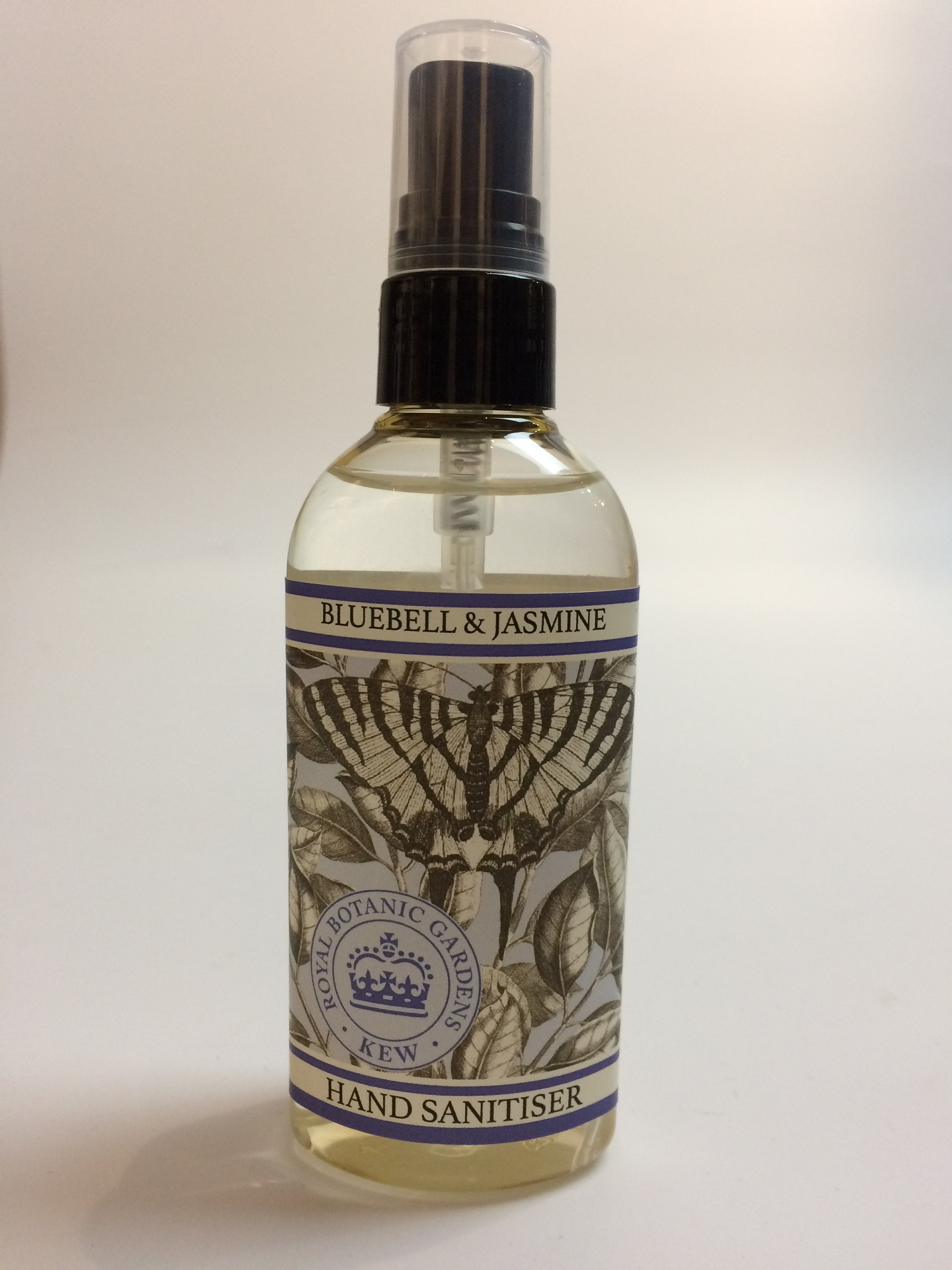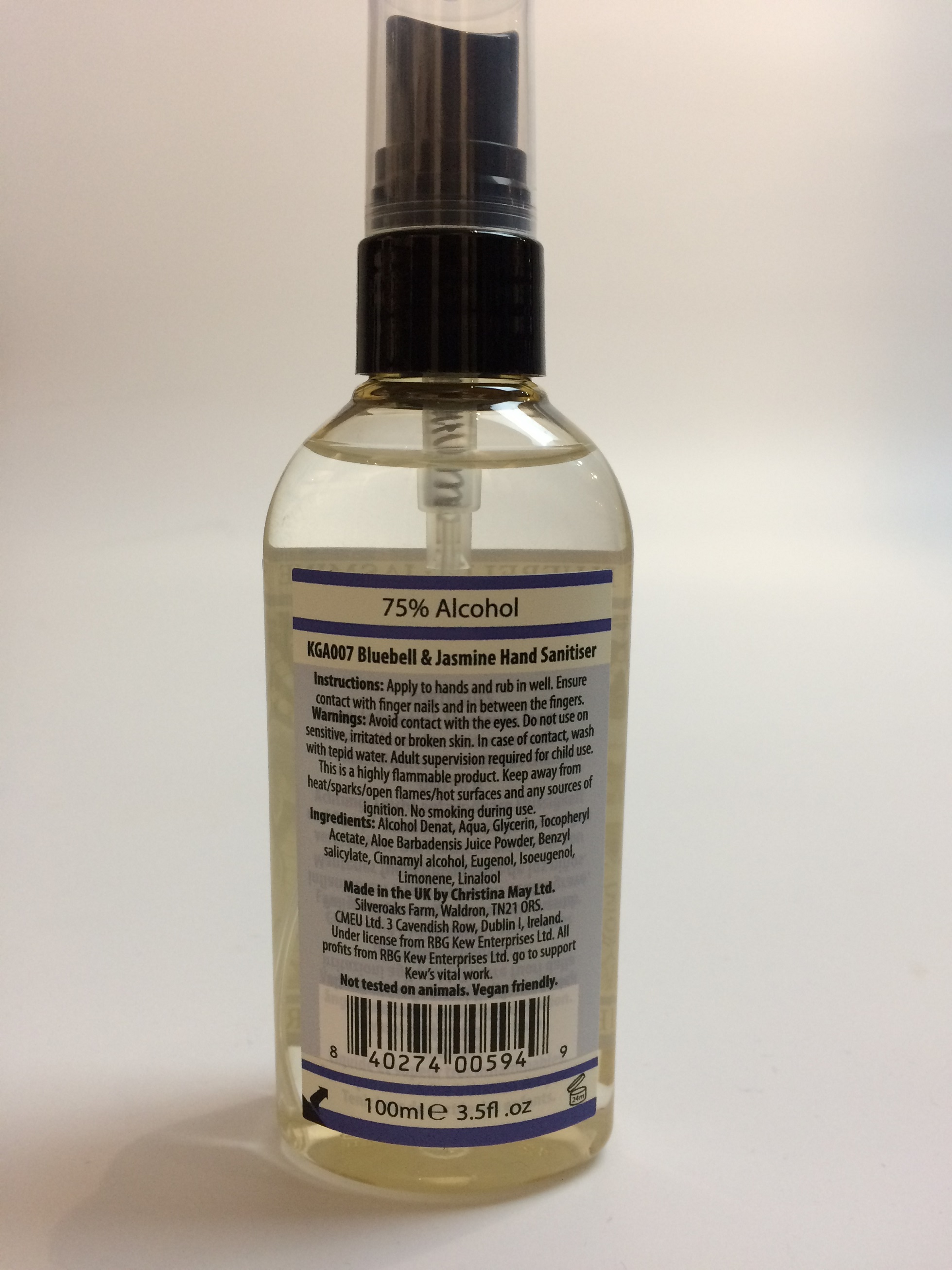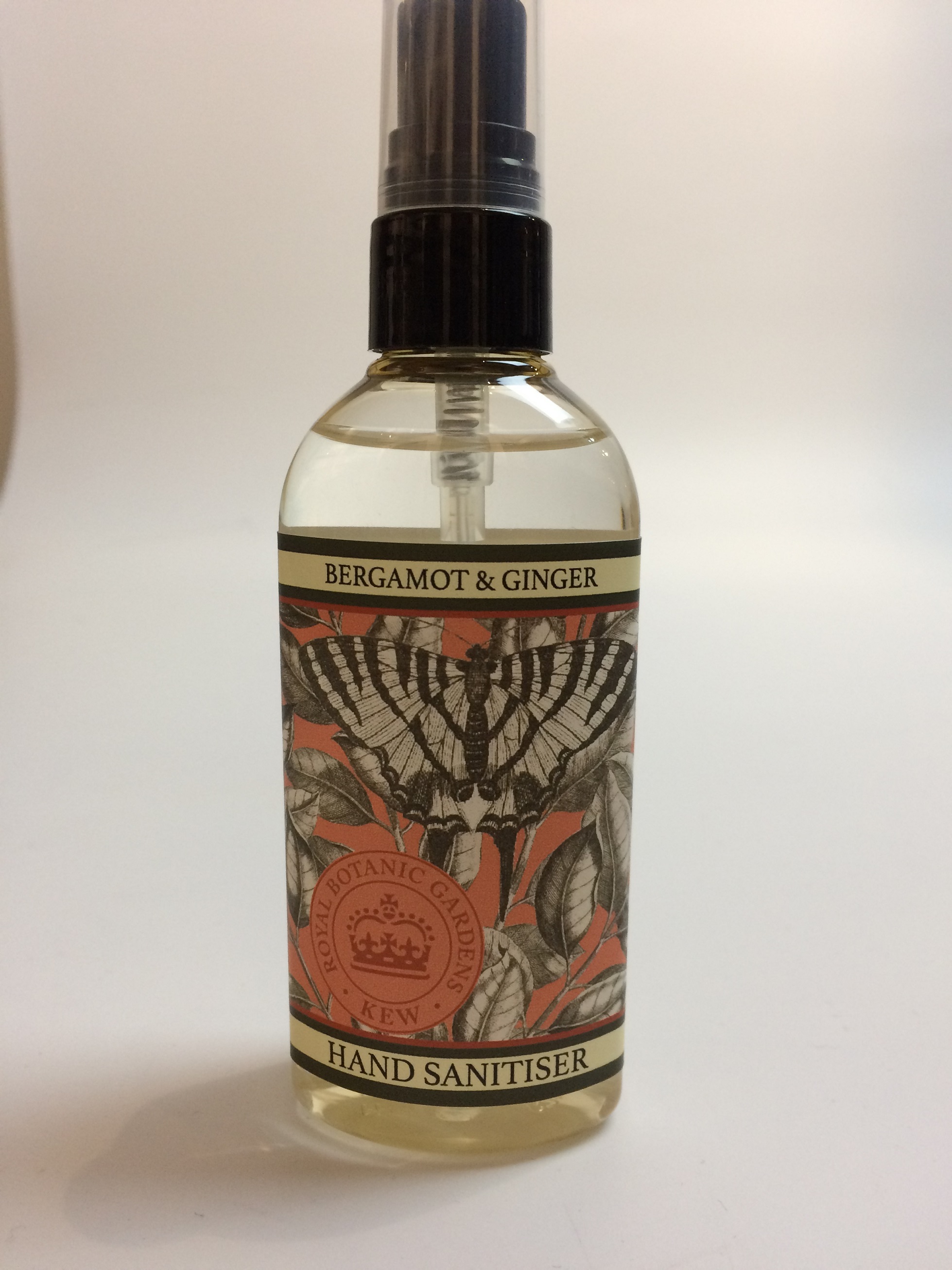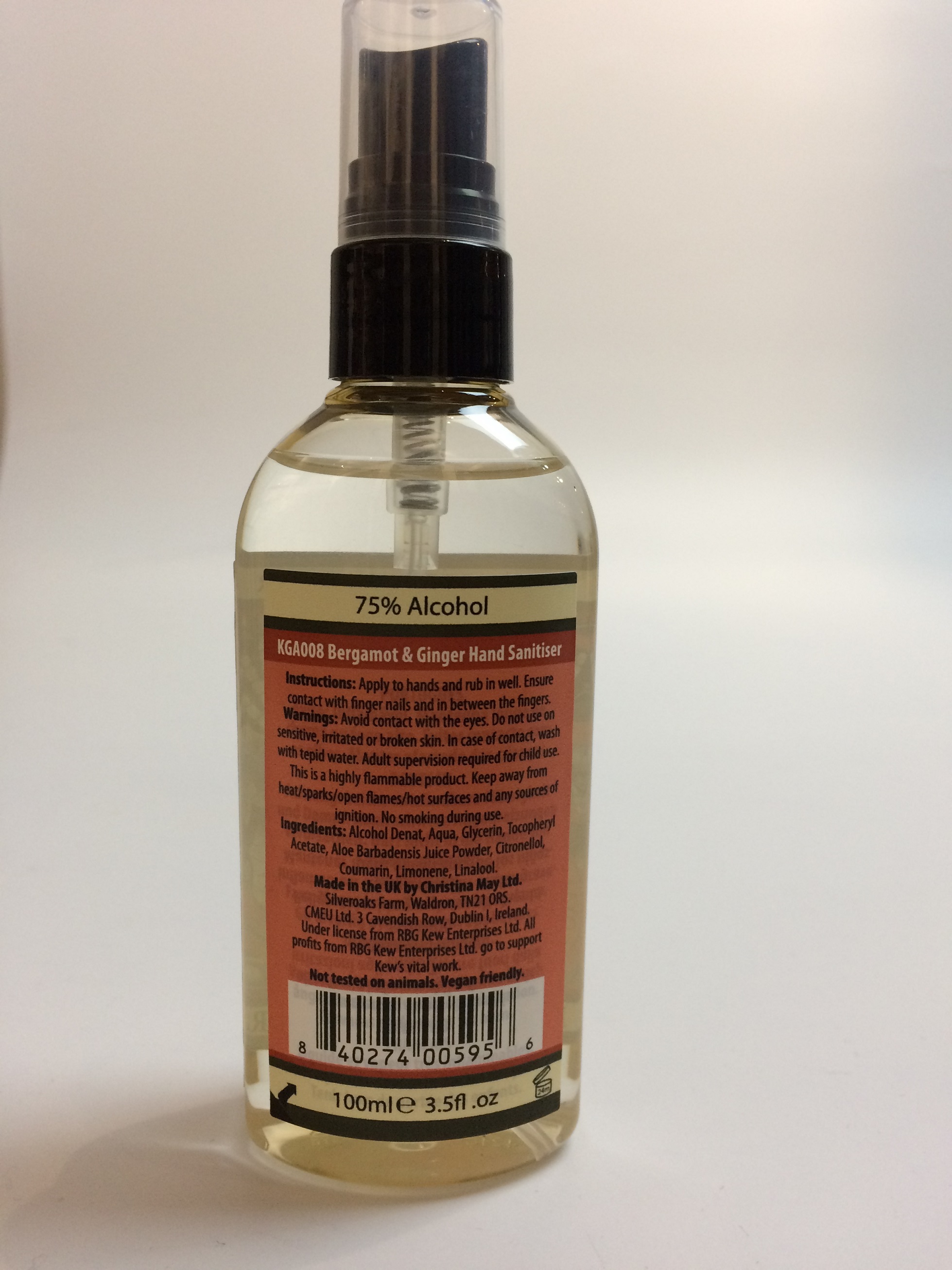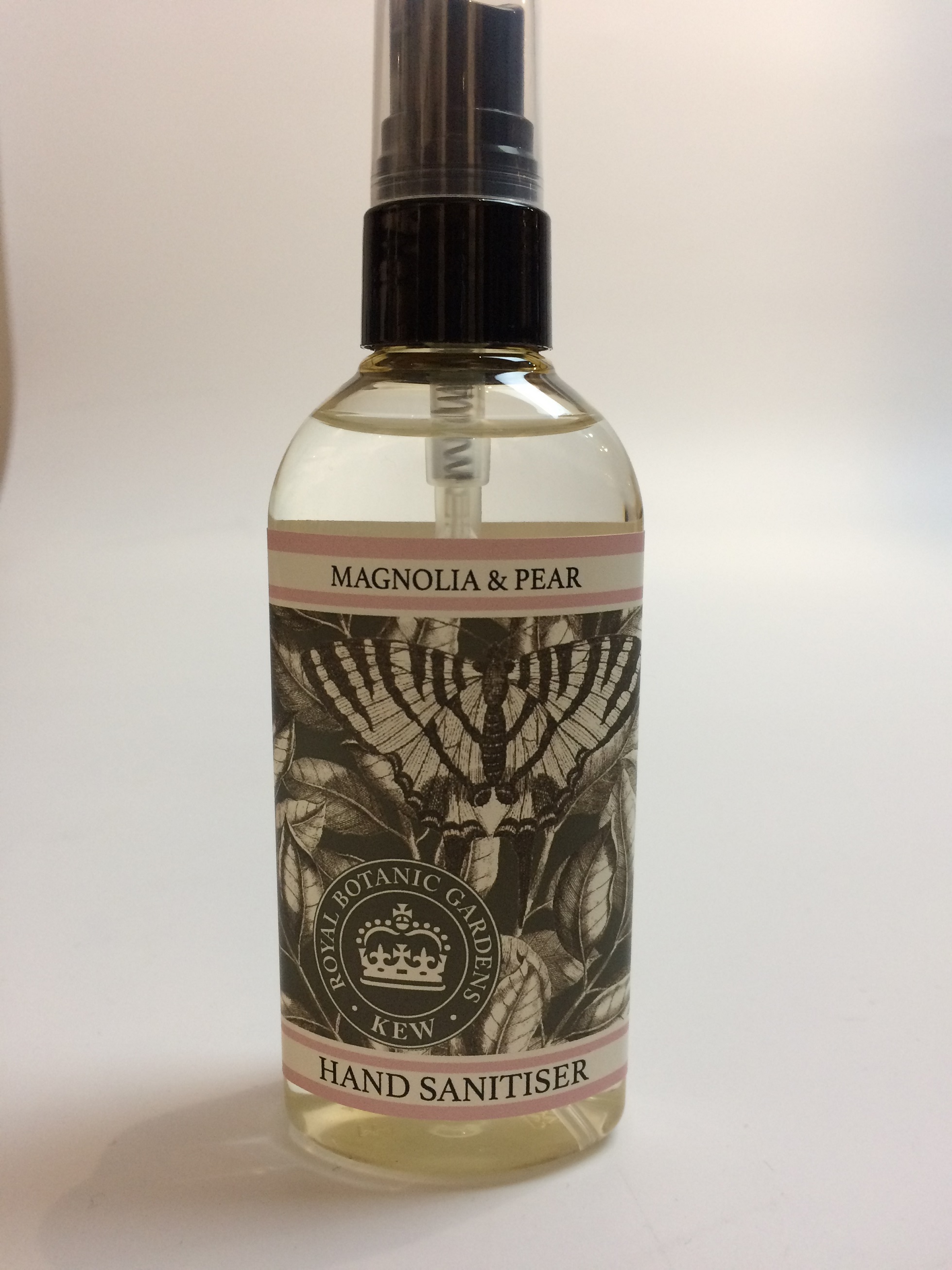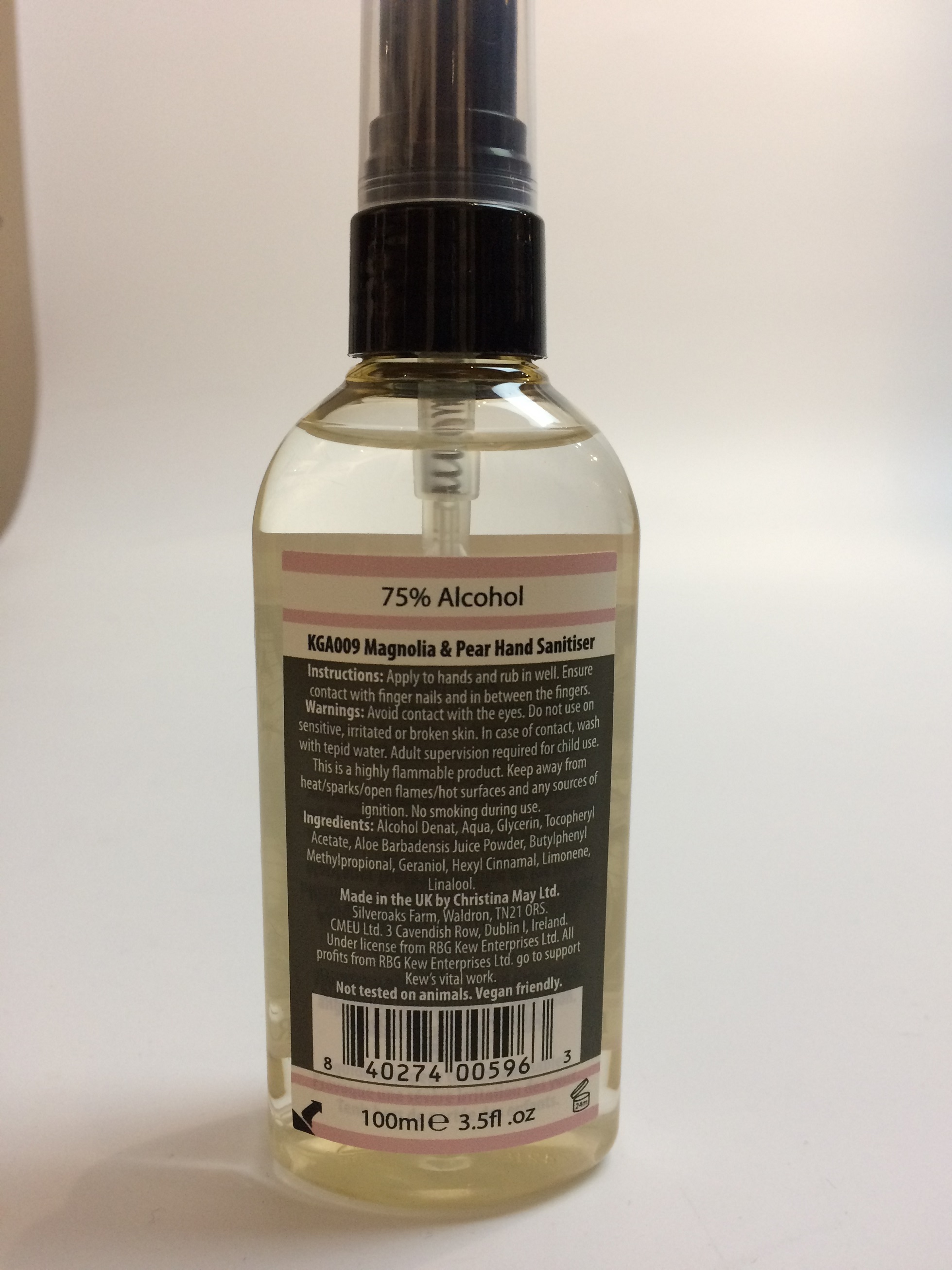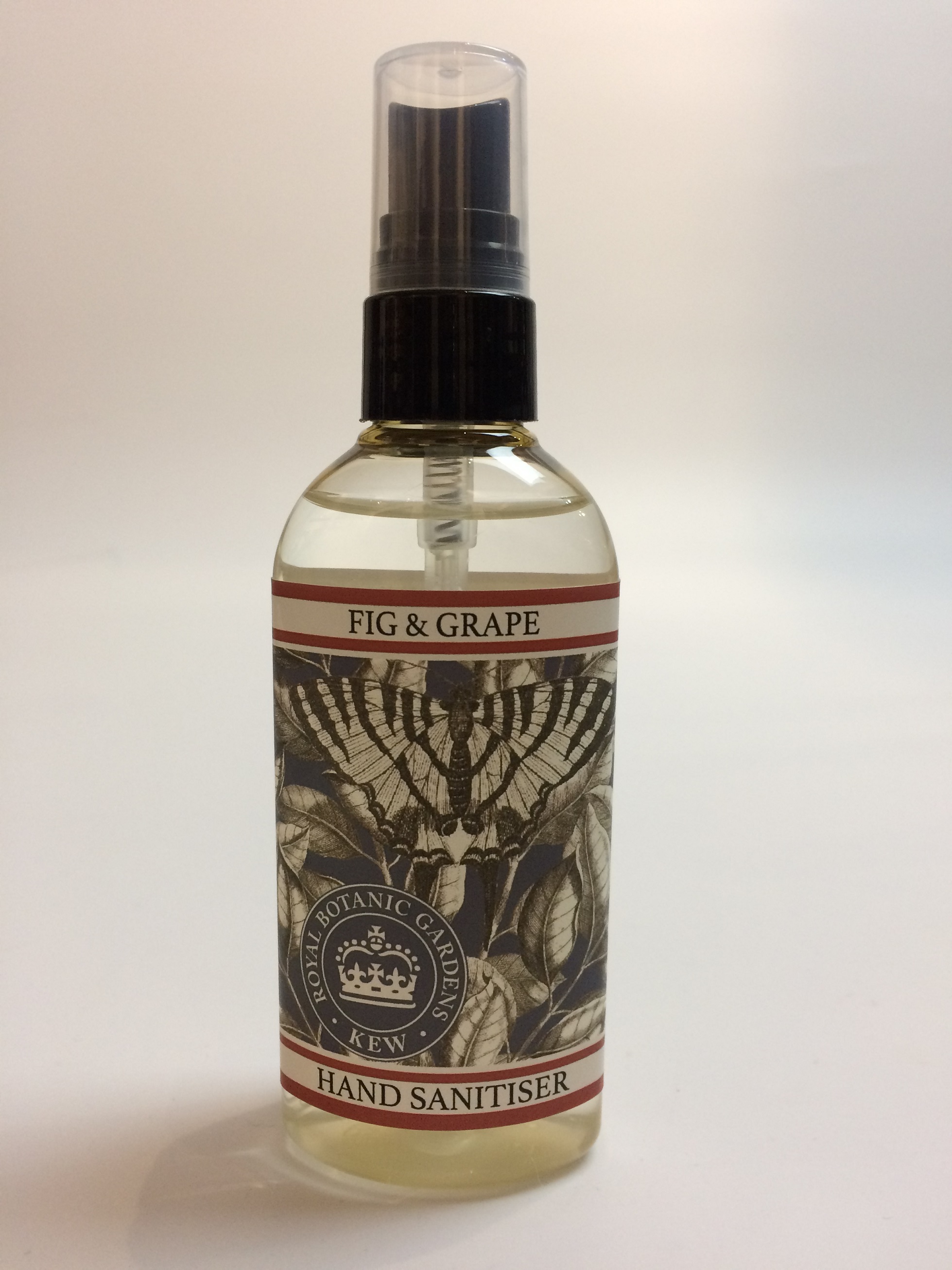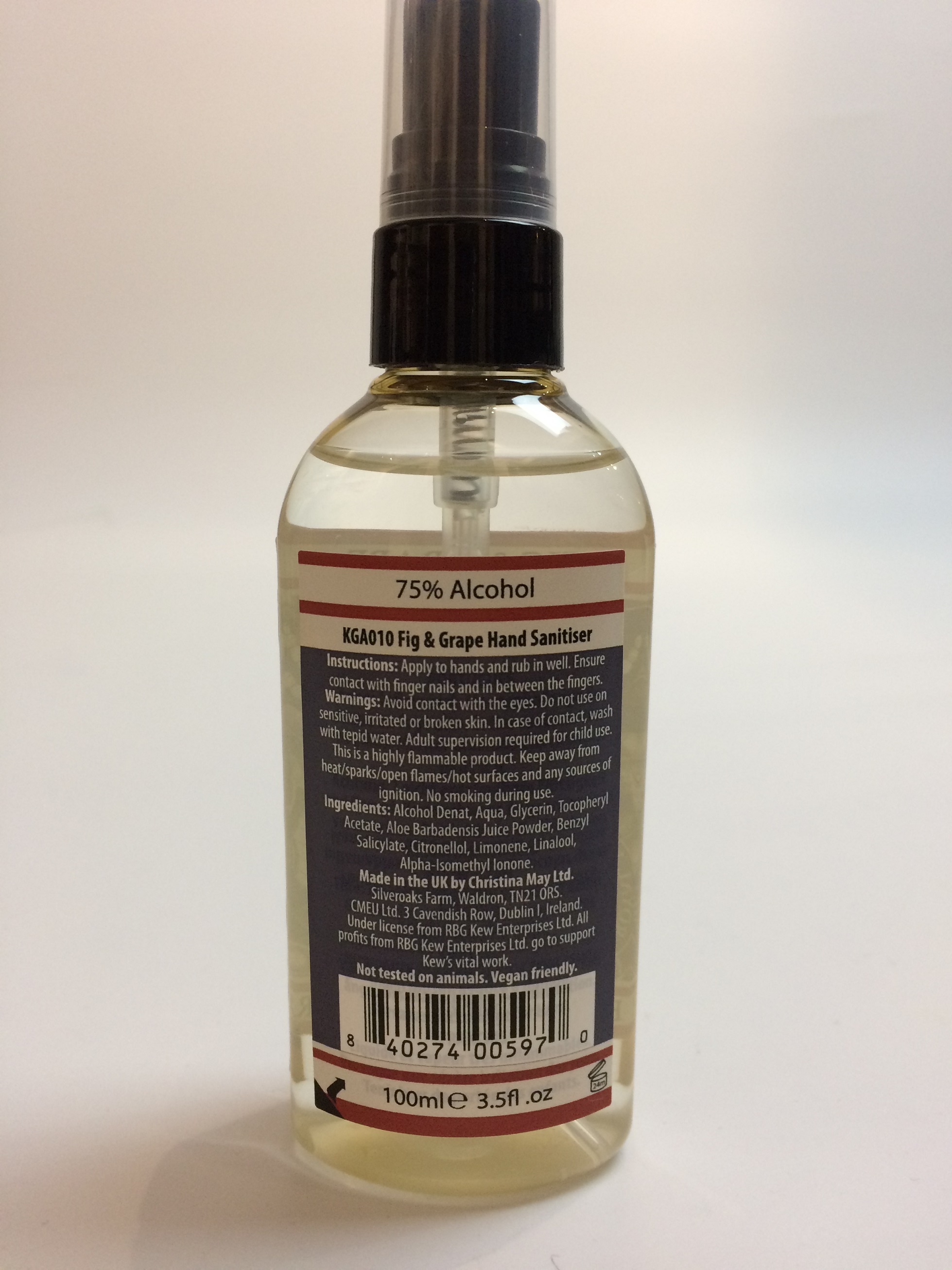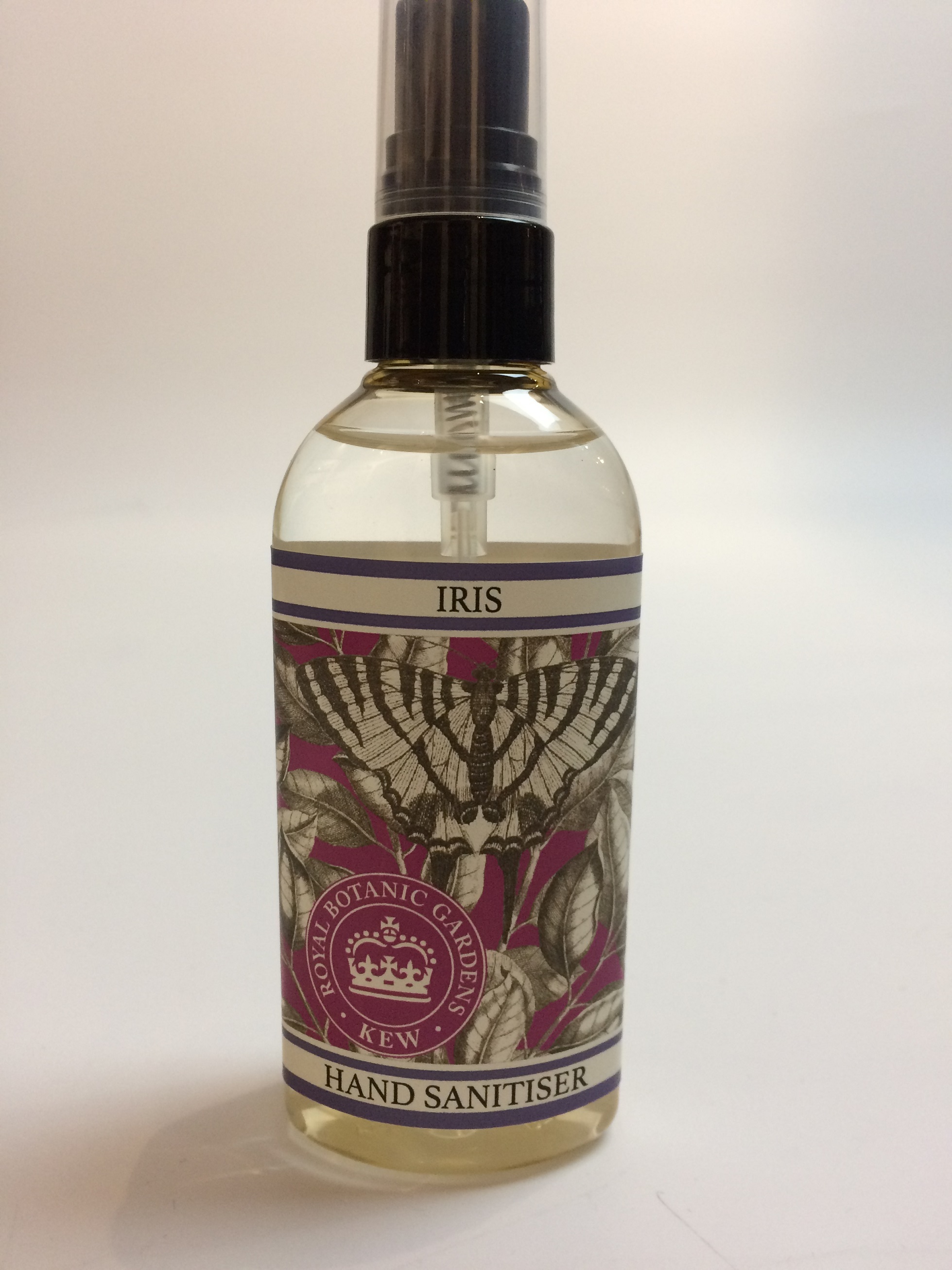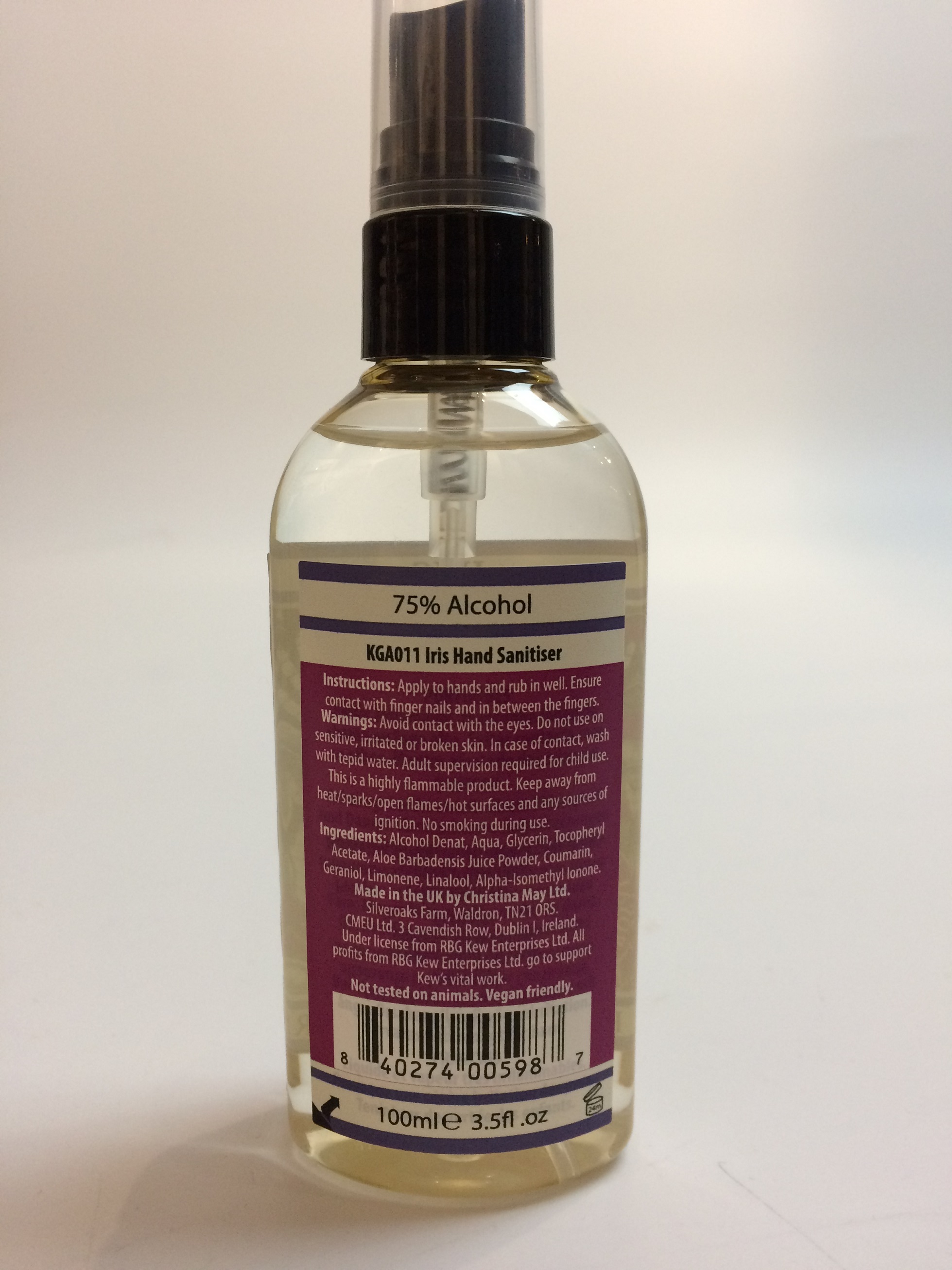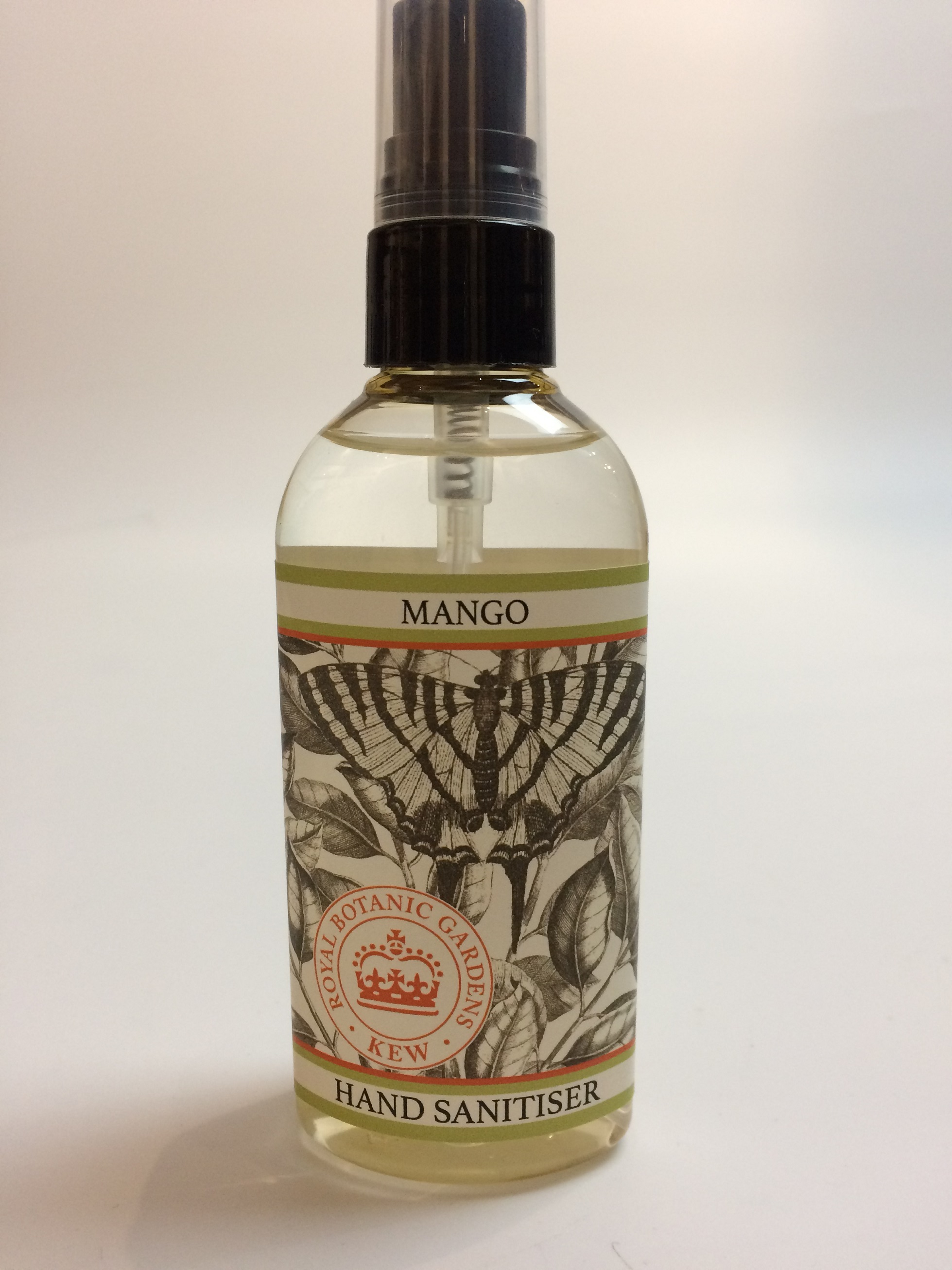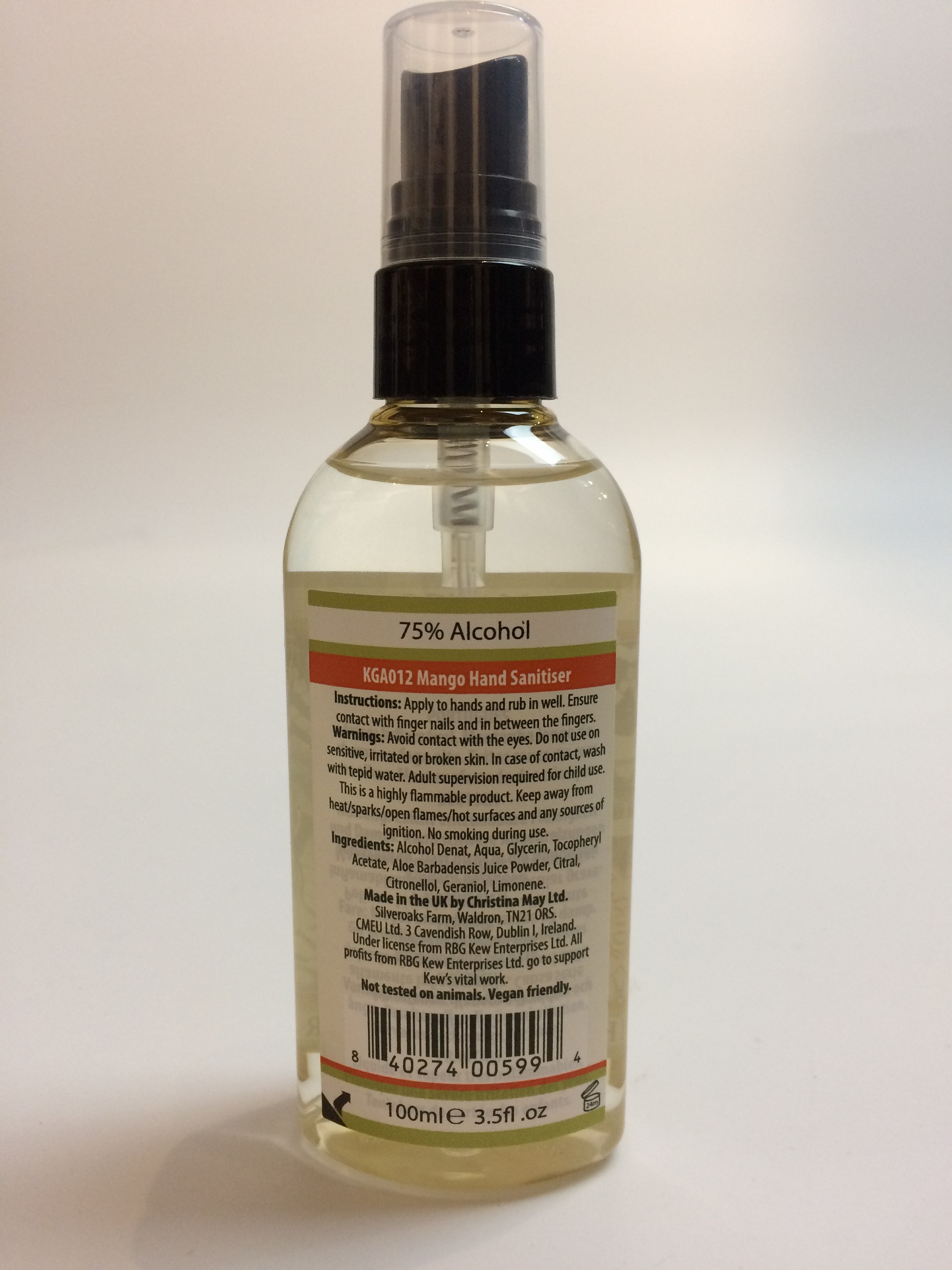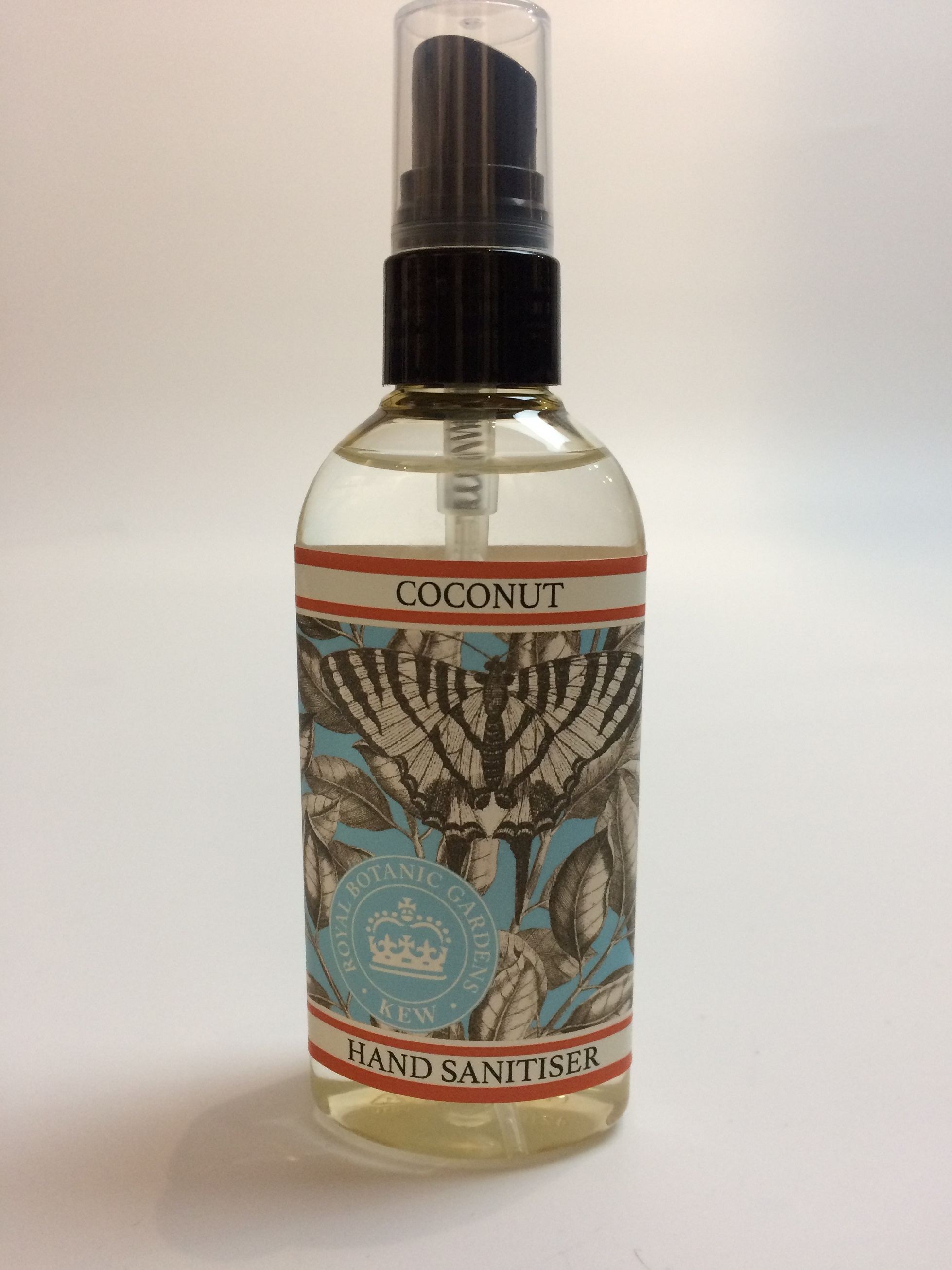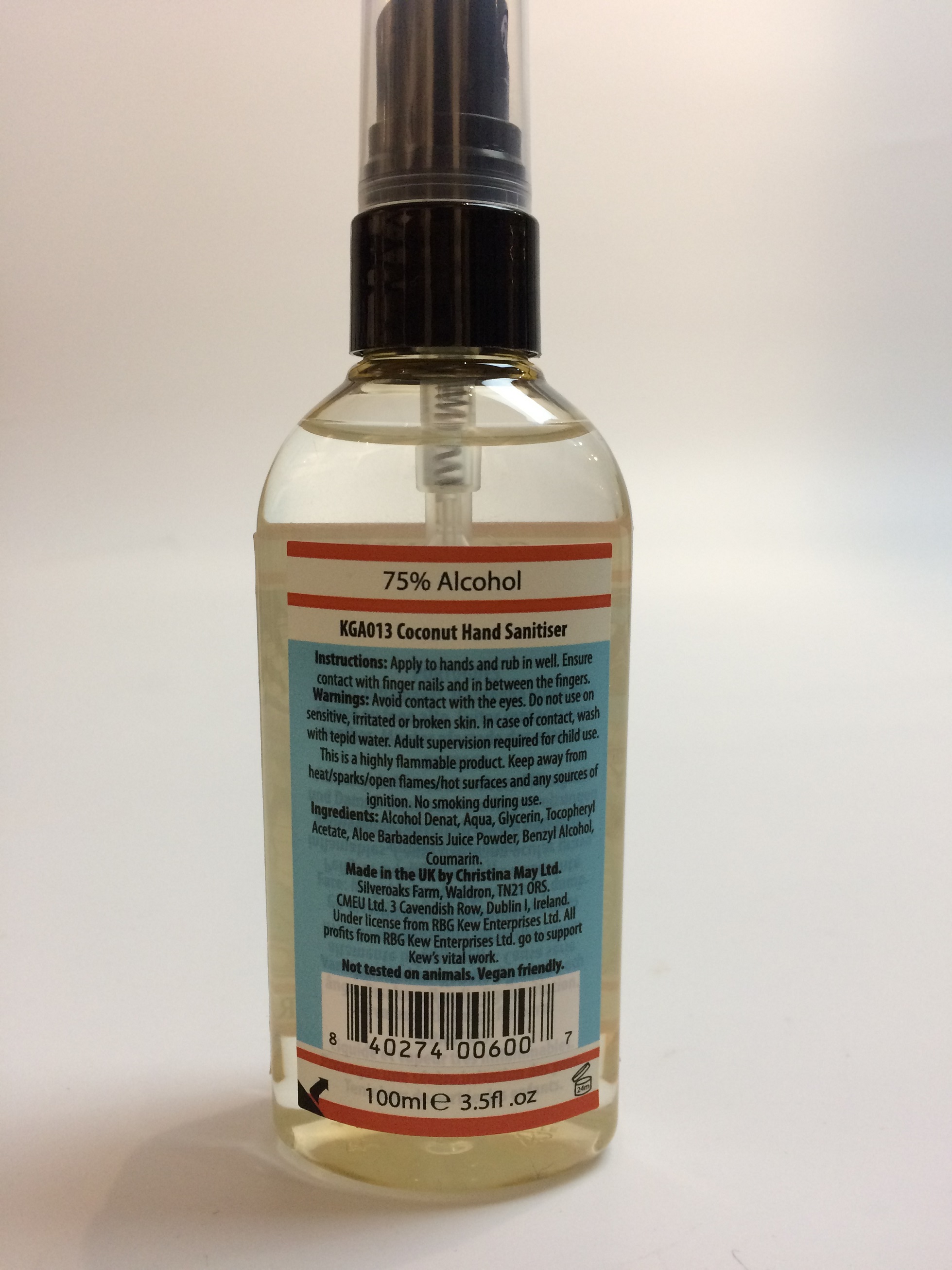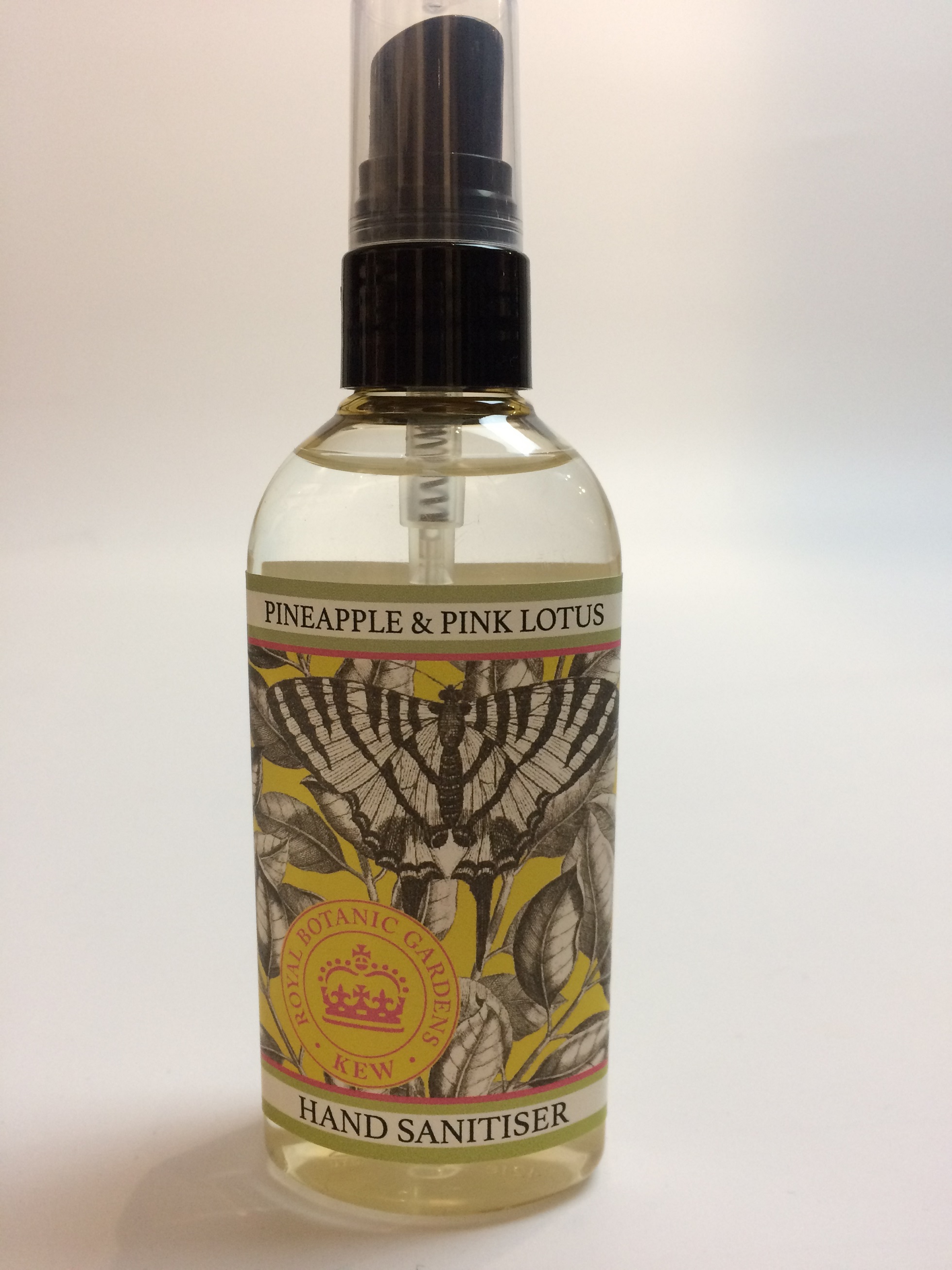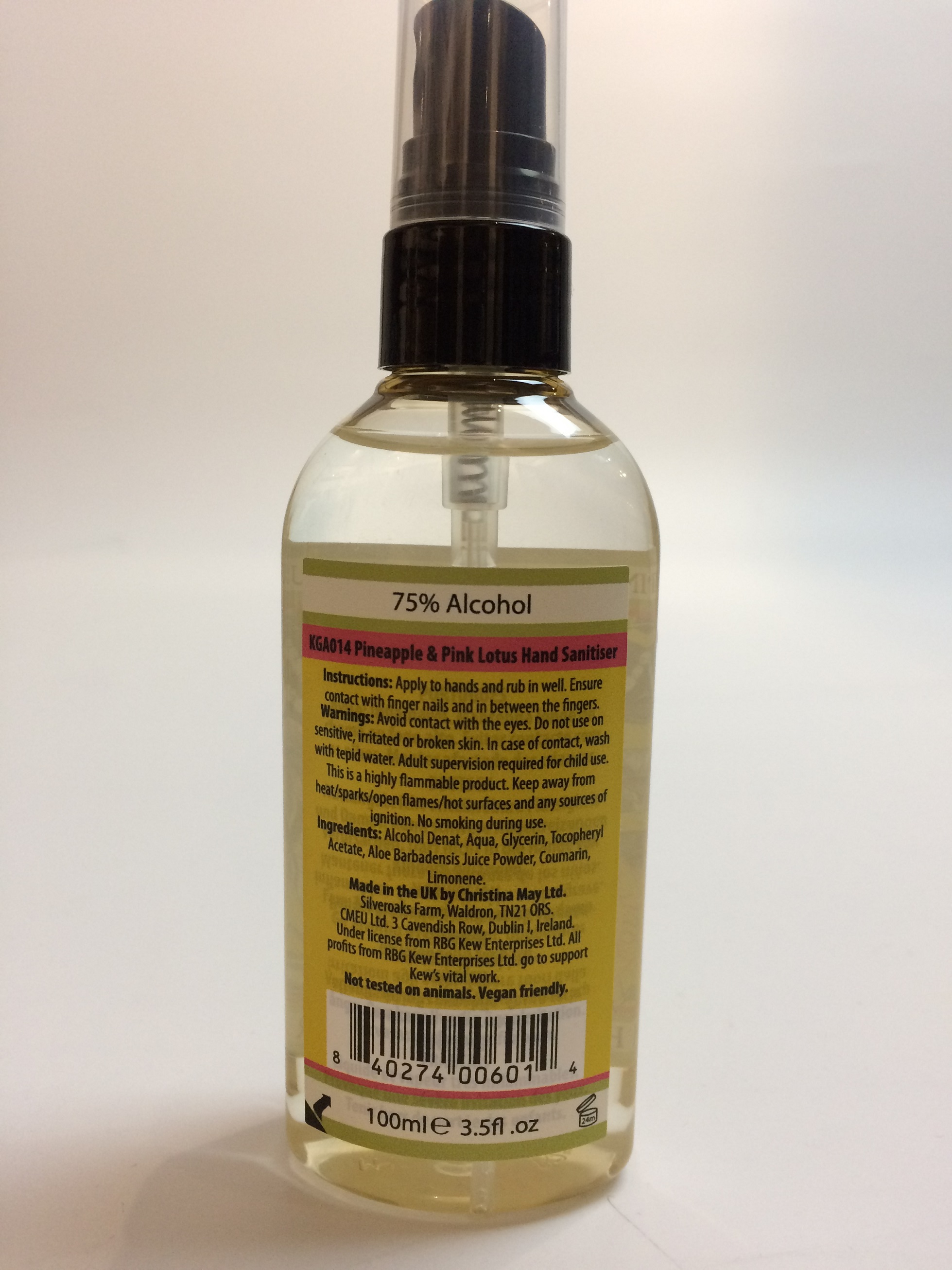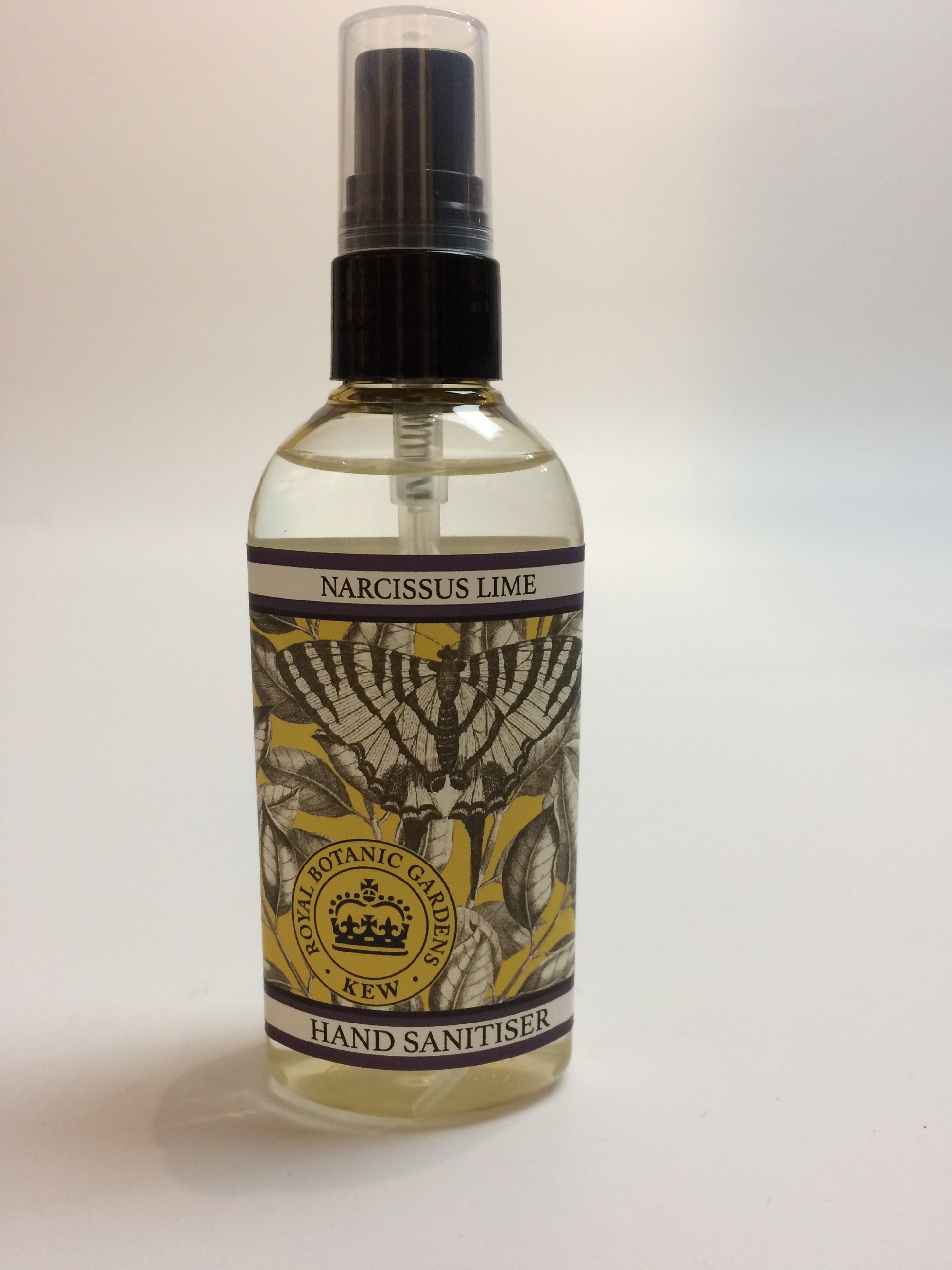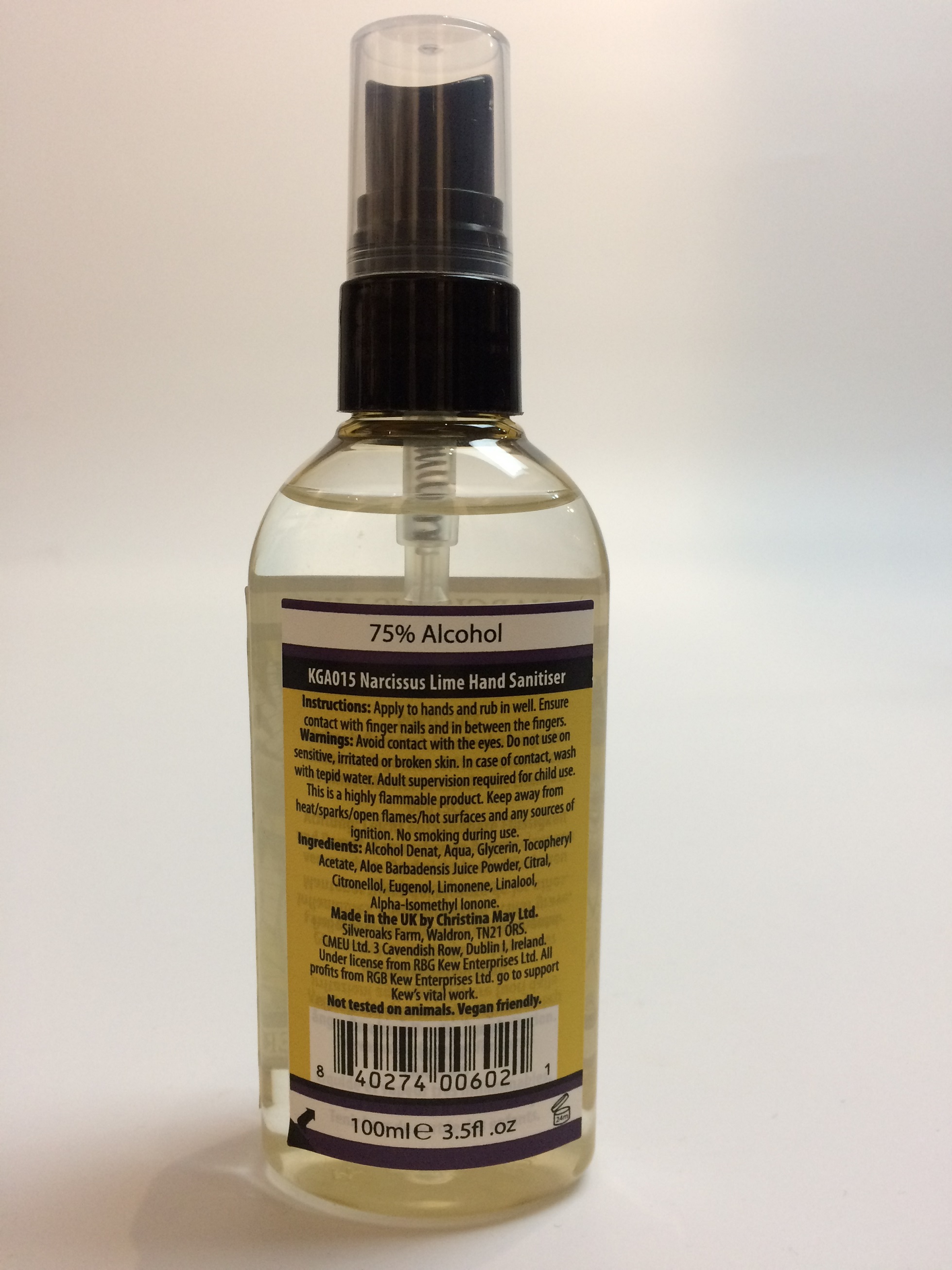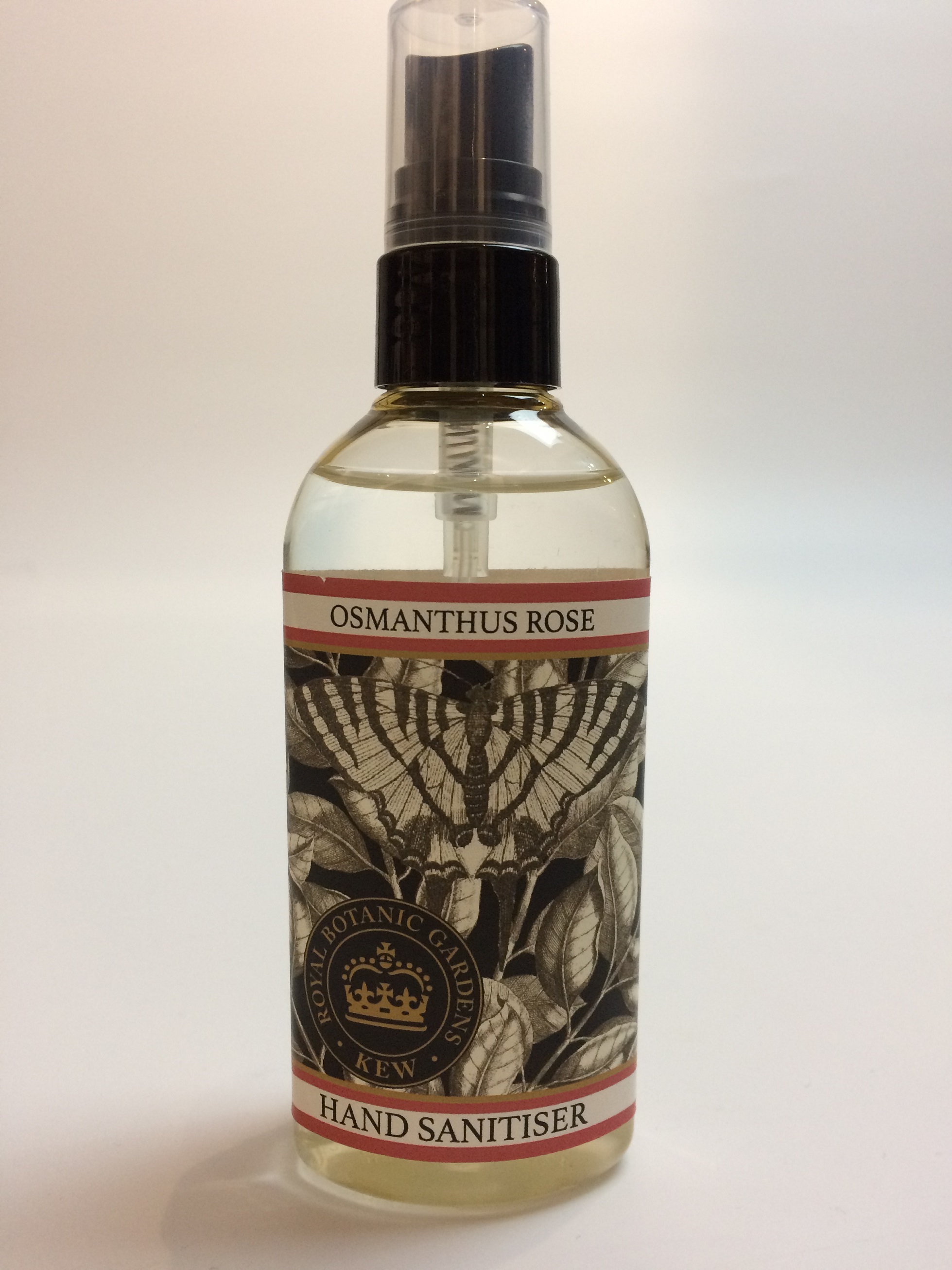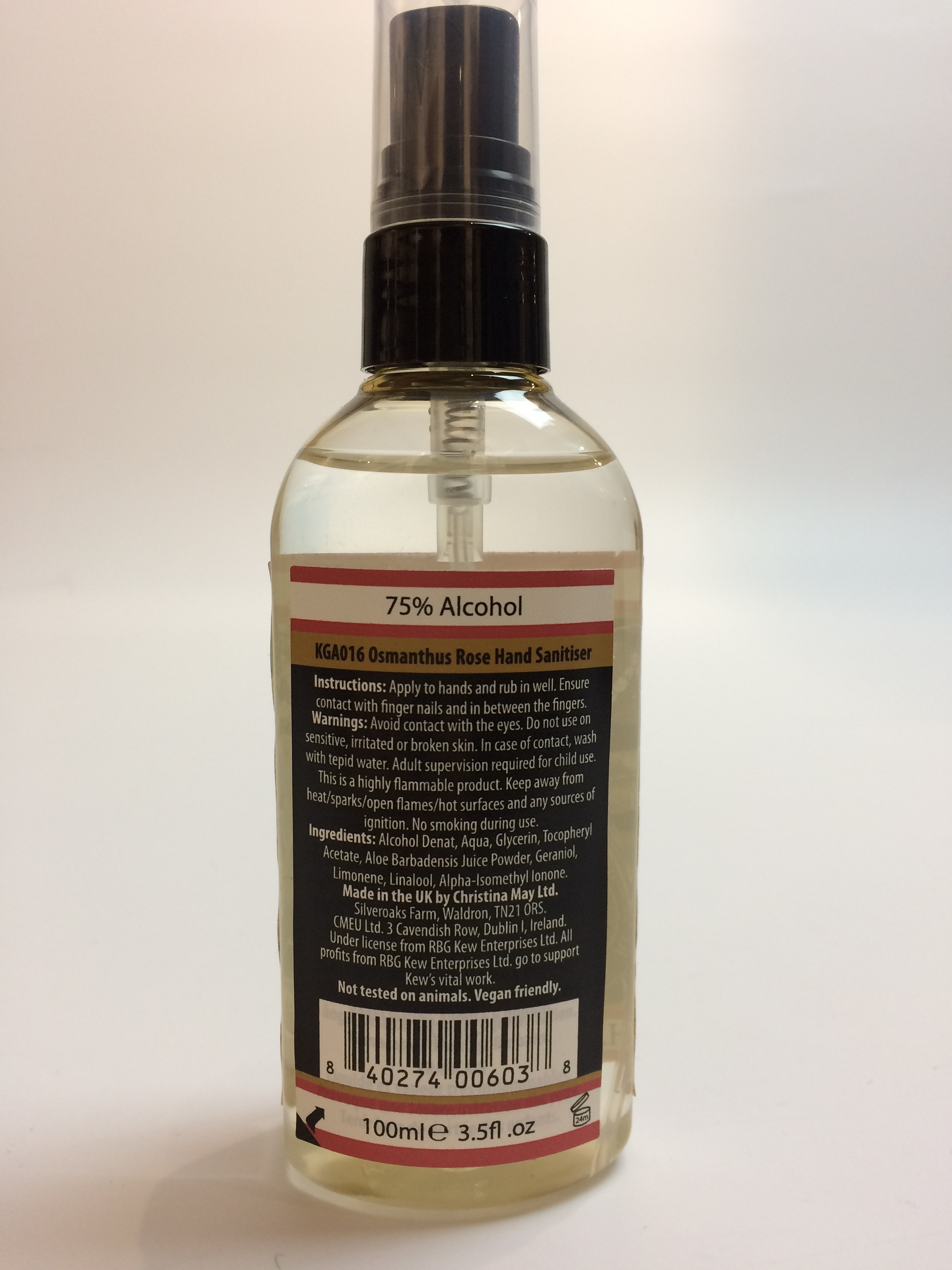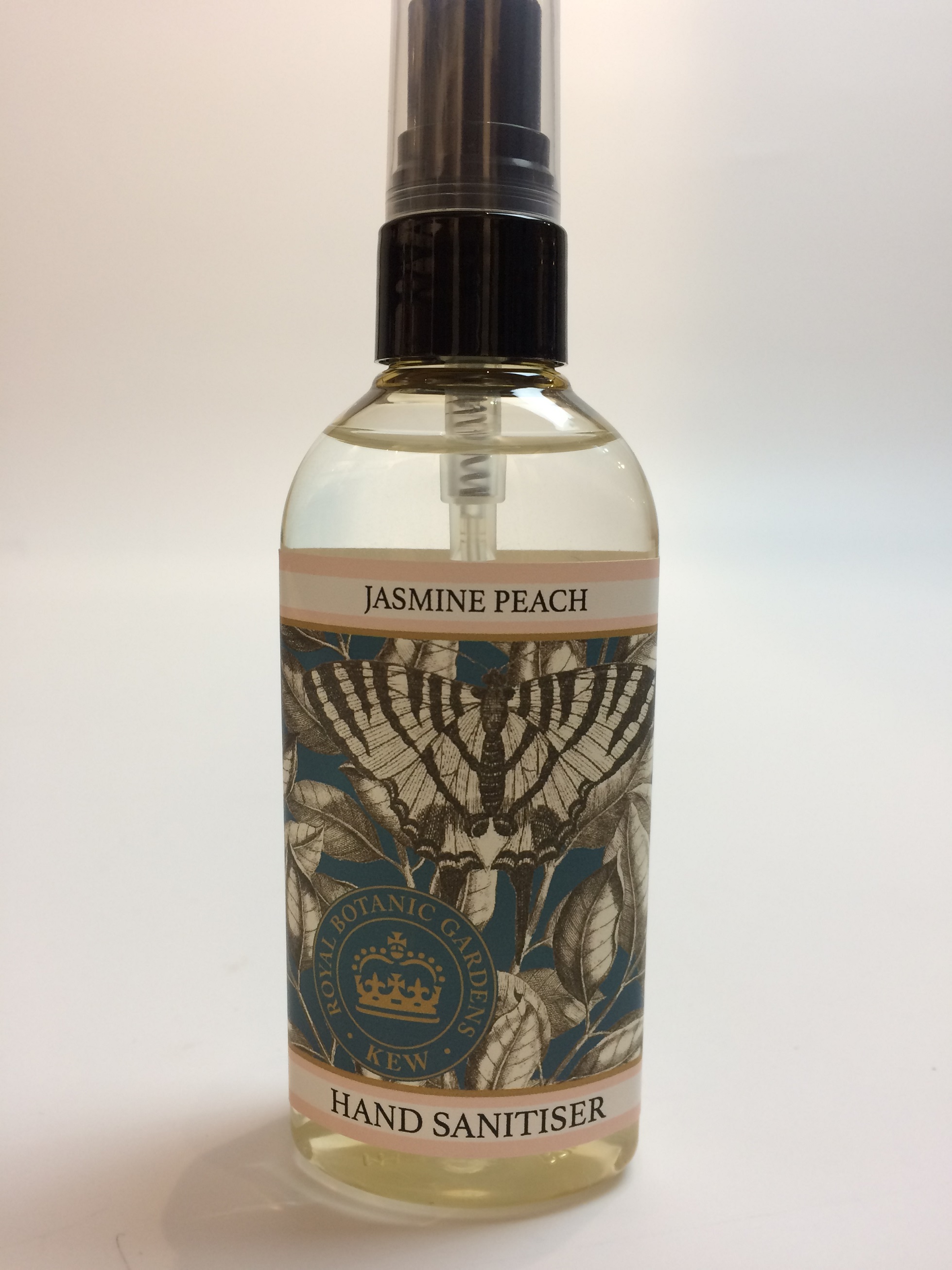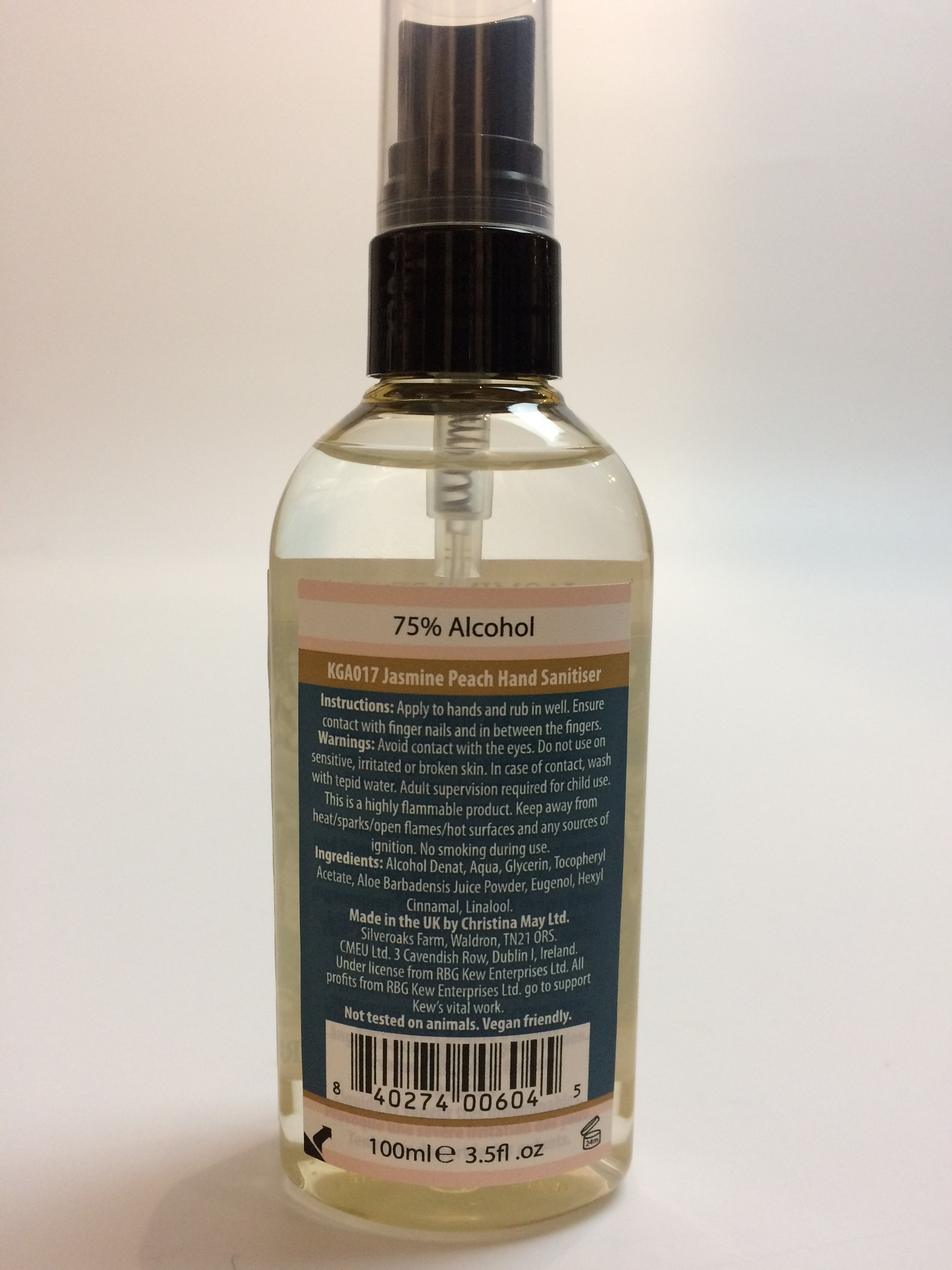 DRUG LABEL: Kew Hand Sanitiser Summer Rose
NDC: 81318-002 | Form: SPRAY
Manufacturer: Christina May Ltd
Category: otc | Type: HUMAN OTC DRUG LABEL
Date: 20210104

ACTIVE INGREDIENTS: ALCOHOL 78 mL/78 mL
INACTIVE INGREDIENTS: .ALPHA.-TOCOPHEROL ACETATE; ALOE VERA LEAF; GLYCERIN; WATER

Active Ingredient(s)

Alcohol 75% v/v. Purpose: Antiseptic

Purpose

Antiseptic, Hand Sanitizer

Use

Hand Sanitizer to help reduce bacteria that potentially can cause disease. For use when soap and water are not available.

Warnings

For external use only. Flammable. Keep away from heat or flame

Do not use

- in children less than 2 months of age
- on open skin wounds

When using this product keep out of eyes, ears, and mouth. In case of contact with eyes, rinse eyes thoroughly with water.
Stop use and ask a doctor if irritation or rash occurs. These may be signs of a serious condition.
Keep out of reach of children. If swallowed, get medical help or contact a Poison Control Center right away.

Stop use and ask a doctor if irritation or rash occurs. These may be signs of a serious condition.

Keep out of reach of children. If swallowed, get medical help or contact a Poison Control Center right away.

Directions

- Place enough product on hands to cover all surfaces. Rub hands together until dry.
- Supervise children under 6 years of age when using this product to avoid swallowing.

Other information

- Store between 15-30C (59-86F)
- Avoid freezing and excessive heat above 40C (104F)

Inactive ingredients

Aqua, glycerin, parfum, tocopheryl acetate, aloe barbadensis juice powder

Package Label - Principal Display Panel NDC: 81318-001-01

100 mL NDC: 81318-001-01

Package Label - Principal Display Panel NDC: 81318-002-01

100mL NDC: 81318-002-01

Package Label - Principal Display Panel NDC: 81318-003-01

100mL NDC: 81318-003-01

Package Label - Principal Display Panel NDC: 81318-004-01

100mL NDC: 81318-004-01

Package Label - Principal Display Panel NDC: 81318-005-01

100mL NDC: 81318-005-01

Package Label - Principal Display Panel NDC: 81318-006-01

100mL NDC: 81318-006-01

Package Label - Principal Display Panel NDC: 81318-007-01

100mL NDC: 81318-007-01

Package Label - Principal Display Panel NDC: 81318-008-01

100mL NDC: 81318-008-01

Package Label - Principal Display Panel NDC: 81318-009-01

100mL NDC: 81318-009-01

Package Label - Principal Display Panel NDC: 81318-010-01

100mL NDC: 81318-010-01

Package Label - Principal Display Panel NDC: 81318-011-01

100mL NDC: 81318-011-01

Package Label - Principal Display Panel NDC: 81318-012-01

100mL NDC: 81318-012-01

Package Label - Principal Display Panel NDC: 81318-013-01

100mL NDC: 81318-013-01

Package Label - Principal Display Panel NDC: 81318-014-01

100mL NDC: 81318-014-01

Package Label - Principal Display Panel NDC: 81318-015-01

100mL NDC: 81318-015-01

Package Label - Principal Display Panel NDC: 81318-016-01

100mL NDC: 81318-016-01

Package Label - Principal Display Panel NDC: 81318-017-01

100mL NDC: 81318-017-01